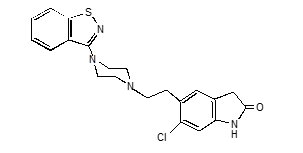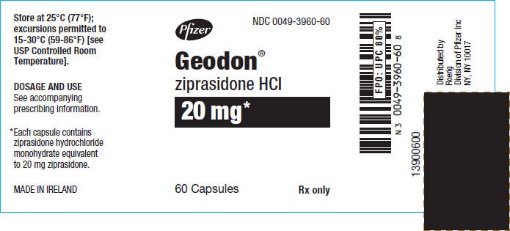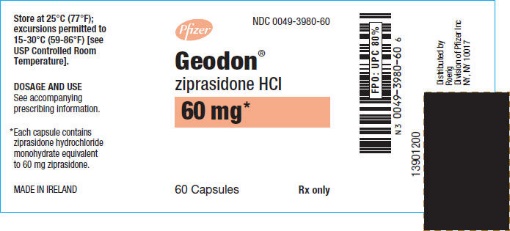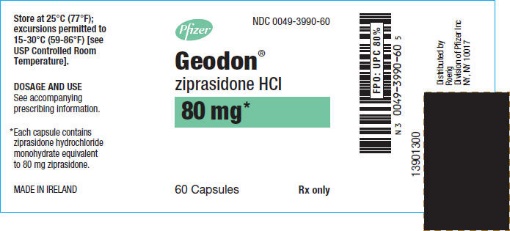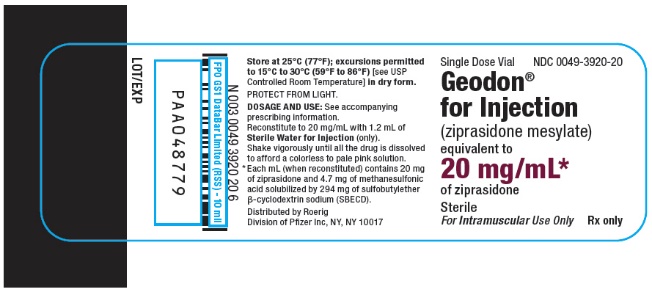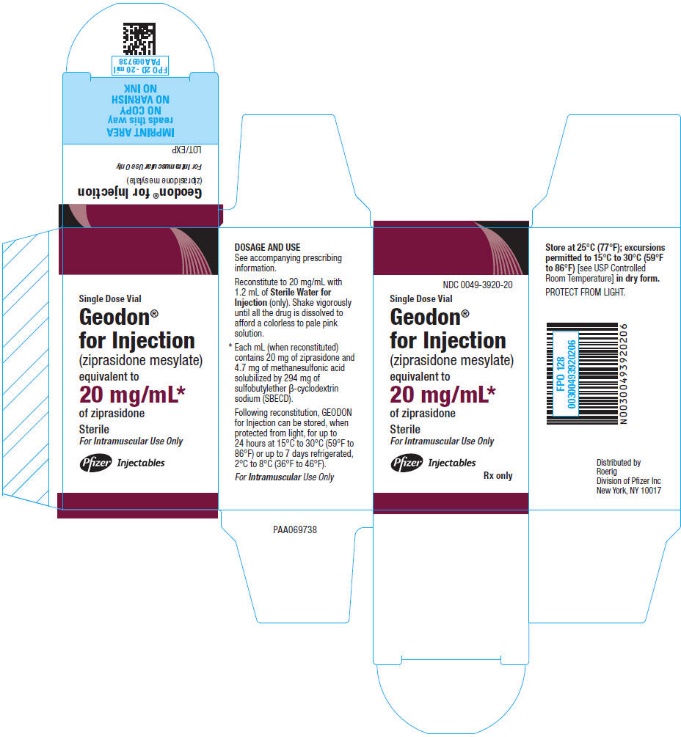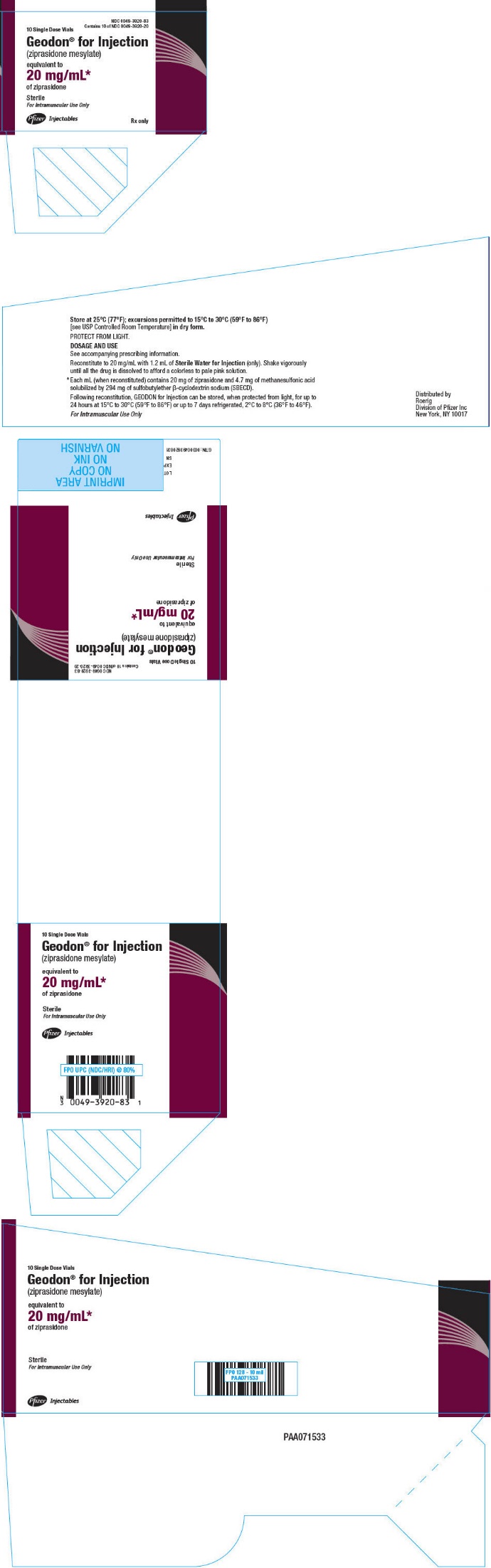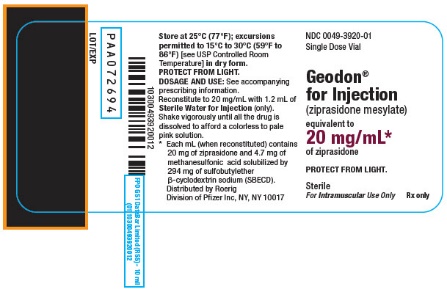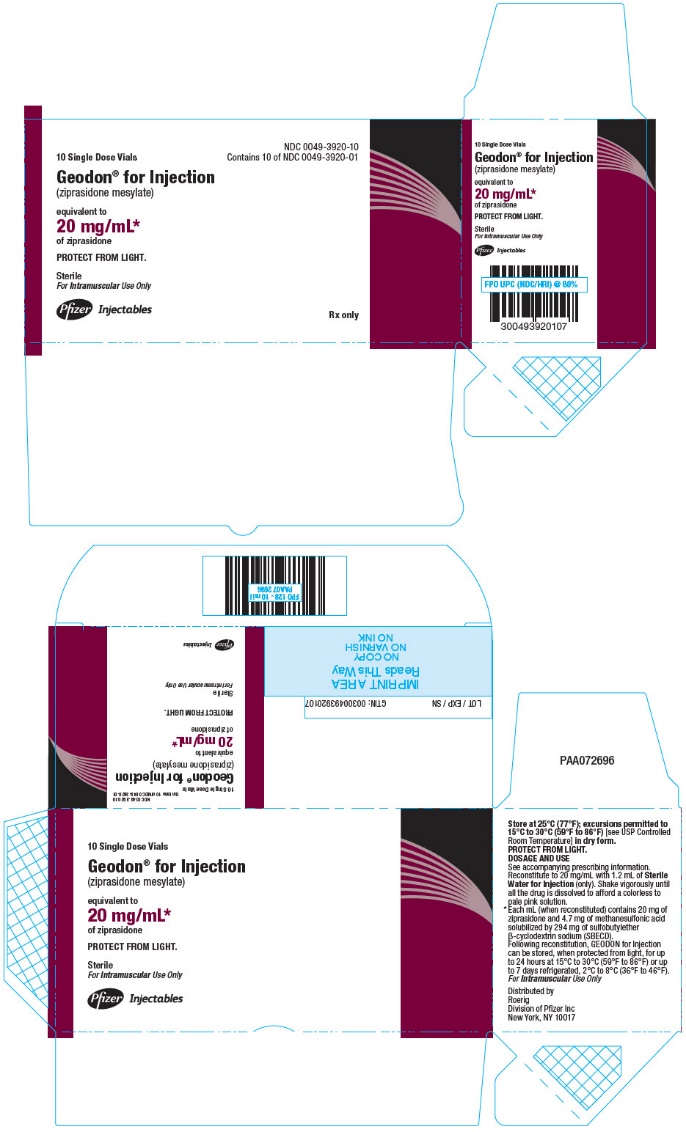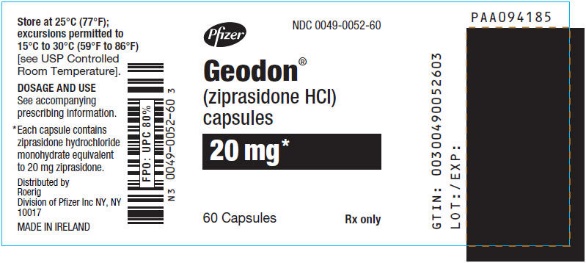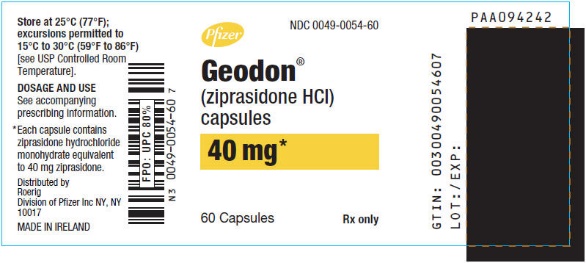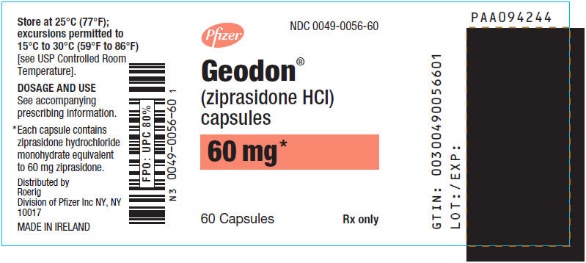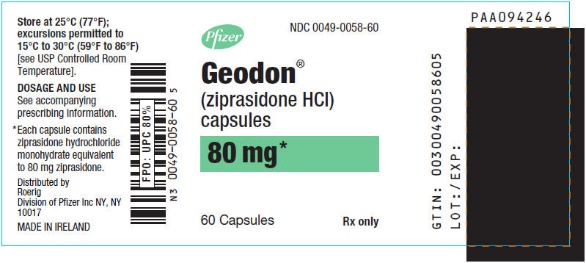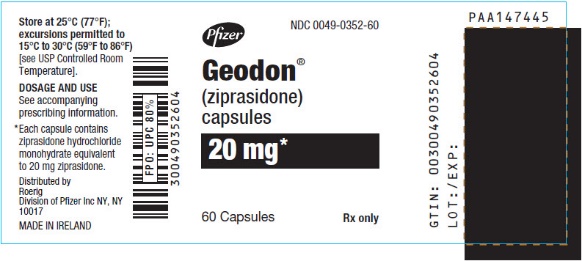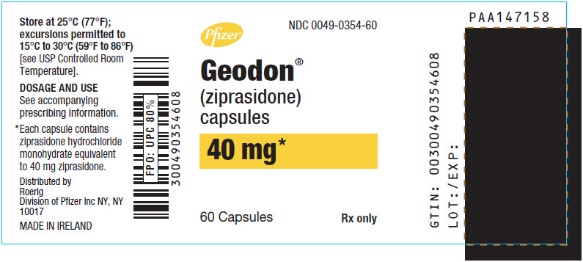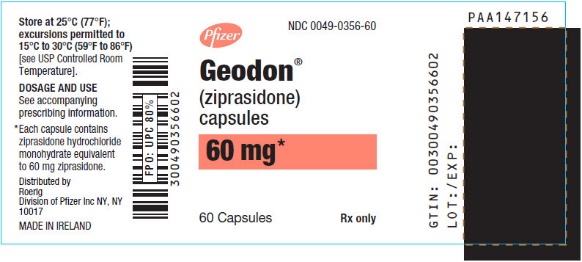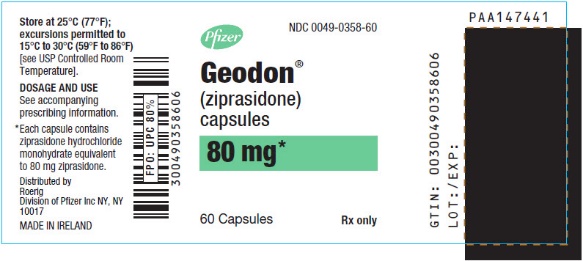 DRUG LABEL: Geodon
NDC: 0049-3960 | Form: CAPSULE
Manufacturer: ROERIG
Category: prescription | Type: HUMAN PRESCRIPTION DRUG LABEL
Date: 20250113

ACTIVE INGREDIENTS: ZIPRASIDONE HYDROCHLORIDE 20 mg/1 1
INACTIVE INGREDIENTS: LACTOSE, UNSPECIFIED FORM; MAGNESIUM STEARATE; STARCH, CORN

HIGHLIGHTS OF PRESCRIBING INFORMATION

These highlights do not include all the information needed to use GEODON safely and effectively. See full prescribing information for GEODON.
GEODON® (ziprasidone) capsules, for oral use
GEODON® (ziprasidone mesylate) for injection, for intramuscular use
Initial U.S. Approval: 2001

RECENT MAJOR CHANGES

Dosage and Administration (2.5) 1/2025
Contraindications (4) 1/2025
Warnings and Precautions (5.4, 5.15) 1/2025

WARNING: INCREASED MORTALITY IN ELDERLY PATIENTS WITH DEMENTIA-RELATED PSYCHOSIS

See full prescribing information for complete boxed warning.

Elderly patients with dementia-related psychosis treated with antipsychotic drugs are at an increased risk of death. GEODON is not approved for the treatment of patients with dementia-related psychosis. (5.1)

1 INDICATIONS AND USAGE

GEODON is an atypical antipsychotic. In choosing among treatments, prescribers should be aware of the capacity of GEODON to prolong the QT interval and may consider the use of other drugs first. (1)

GEODON capsules are indicated for the:

- treatment of schizophrenia in adults. (1)
- acute treatment of adults as monotherapy of manic or mixed episodes associated with bipolar I disorder. (1)
- maintenance treatment of bipolar I disorder as an adjunct to lithium or valproate in adults. (1)

GEODON for injection is indicated for the:

- acute treatment of agitation in schizophrenic patients in adults. (1)

2 DOSAGE AND ADMINISTRATION

- Administer capsules orally with food. Do not open, crush, or chew. (2.1)
- Schizophrenia: Initiate at 20 mg twice daily. Daily dosage may be adjusted up to 80 mg twice daily. Dose adjustments should occur at intervals of not less than 2 days. Safety and efficacy has been demonstrated in doses up to 100 mg twice daily. The lowest effective dose should be used. (2.2)
- Acute treatment of manic/mixed episodes of bipolar I disorder: Initiate at 40 mg twice daily. Increase to 60 mg or 80 mg twice daily on day 2 of treatment. Subsequent dose adjustments should be based on tolerability and efficacy within the range of 40-80 mg twice daily. (2.3)
- Maintenance treatment of bipolar I disorder as an adjunct to lithium or valproate: Continue treatment at the same dose on which the patient was initially stabilized, within the range of 40-80 mg twice daily. (2.3)
- Acute treatment of agitation associated with schizophrenia (intramuscular administration): 10 mg-20 mg up to a maximum dose of 40 mg per day. Doses of 10 mg may be administered every 2 hours. Doses of 20 mg may be administered every 4 hours. (2.4)

3 DOSAGE FORMS AND STRENGTHS

- Capsules: 20 mg, 40 mg, 60 mg, and 80 mg (3)
- For injection: 20 mg/mL single-dose vials (3)

4 CONTRAINDICATIONS

- Do not use in patients with a known history of QT prolongation (4.1)
- Do not use in patients with recent acute myocardial infarction (4.1)
- Do not use in patients with uncompensated heart failure (4.1)
- Do not use in combination with other drugs that have demonstrated QT prolongation (4.1)
- Do not use in patients with known hypersensitivity to ziprasidone (4.2)
- Concomitant use of monoamine oxidase inhibitors (MAOIs), or use within 14 days of stopping MAOIs. (4.3)

5 WARNINGS AND PRECAUTIONS

- Cerebrovascular Adverse Reactions in Elderly Patients with Dementia-Related Psychosis: Increased incidence of cerebrovascular adverse reactions (e.g., stroke, transient ischemic attack). (5.2)
- QT Interval Prolongation: GEODON use should be avoided in patients with bradycardia, hypokalemia or hypomagnesemia, congenital prolongation of the QT interval, or in combination with other drugs that have demonstrated QT prolongation. (5.3)
- Serotonin Syndrome: Increased risk when co-administered with other serotonergic agents, but also when taken alone. If it occurs, discontinue GEODON and serotonergic agents and initiate supportive treatment. (5.4)
- Neuroleptic Malignant Syndrome (NMS): Potentially fatal symptom complex has been reported with antipsychotic drugs. Manage with immediate discontinuation of drug and close monitoring. (5.5)
- Severe Cutaneous Adverse Reactions, such as Drug Reaction with Eosinophilia and Systemic Symptoms (DRESS) and Stevens-Johnson syndrome has been reported with ziprasidone exposure. DRESS and other Severe Cutaneous Adverse Reactions (SCAR) are sometimes fatal. Discontinue GEODON if DRESS or SCAR are suspected. (5.6)
- Tardive Dyskinesia: May develop acutely or chronically. (5.7)
- Metabolic Changes: Atypical antipsychotic drugs have been associated with metabolic changes that may increase cardiovascular/ cerebrovascular risk. These metabolic changes include hyperglycemia, dyslipidemia, and weight gain. (5.8)
- Hyperglycemia and Diabetes Mellitus (DM): Monitor all patients for symptoms of hyperglycemia including polydipsia, polyuria, polyphagia, and weakness. Patients with DM risk factors should undergo blood glucose testing before and during treatment. (5.8)
- Dyslipidemia: Undesirable alterations have been observed in patients treated with atypical antipsychotics. (5.8)
- Weight Gain: Weight gain has been reported. Monitor weight gain. (5.8)
- Rash: Discontinue in patients who develop a rash without an identified cause. (5.9)
- Orthostatic Hypotension: Use with caution in patients with known cardiovascular or cerebrovascular disease. (5.10)
- Leukopenia, Neutropenia, and Agranulocytosis has been reported with antipsychotics. Patients with a pre-existing low white blood cell count (WBC) or a history of leukopenia/neutropenia should have their complete blood count (CBC) monitored frequently during the first few months of therapy and should discontinue GEODON at the first sign of a decline in WBC in the absence of other causative factors. (5.12)
- Seizures: Use cautiously in patients with a history of seizures or with conditions that lower seizure threshold. (5.13)
- Potential for Cognitive and Motor Impairment: Patients should use caution when operating machinery. (5.16)
- Suicide: Closely supervise high-risk patients. (5.19)

6 ADVERSE REACTIONS

Commonly observed adverse reactions (incidence ≥5% and at least twice the incidence for placebo) were:

- Schizophrenia: Somnolence, respiratory tract infection. (6.1)
- Manic and Mixed Episodes Associated with Bipolar Disorder: Somnolence, extrapyramidal symptoms, dizziness, akathisia, abnormal vision, asthenia, vomiting. (6.1)
- Intramuscular Administration (≥5% and at least twice the lowest intramuscular ziprasidone group): Headache, nausea, somnolence. (6.1)

To report SUSPECTED ADVERSE REACTIONS, contact Viatris at 1-877-446-3679 (1-877-4-INFO-RX) or FDA at 1-800-FDA-1088 or www.fda.gov/medwatch.

7 DRUG INTERACTIONS

- Ziprasidone should not be used in combination with other drugs that have demonstrated QT prolongation. (4.1, 7.3)
- The absorption of ziprasidone is increased up to two-fold in the presence of food. (7.10)
- The full prescribing information contains additional drug interactions. (7)

8 USE IN SPECIFIC POPULATIONS

- Pregnancy: May cause extrapyramidal and/or withdrawal symptoms in neonates with third trimester exposure. (8.1)
- Renal Impairment: Intramuscular ziprasidone should be administered with caution to patients with impaired renal function as the cyclodextrin excipient is cleared by renal filtration. (8.6)

FULL PRESCRIBING INFORMATION

WARNING: INCREASED MORTALITY IN ELDERLY PATIENTS WITH DEMENTIA-RELATED PSYCHOSIS

Elderly patients with dementia-related psychosis treated with antipsychotic drugs are at an increased risk of death. GEODON is not approved for the treatment of patients with dementia-related psychosis [see Warnings and Precautions (5.1)].

1 INDICATIONS AND USAGE

GEODON is indicated for the treatment of schizophrenia, as monotherapy for the acute treatment of bipolar manic or mixed episodes, and as an adjunct to lithium or valproate for the maintenance treatment of bipolar disorder. GEODON intramuscular is indicated for acute agitation in schizophrenic patients. When deciding among the alternative treatments available for the condition needing treatment, the prescriber should consider the finding of ziprasidone’s greater capacity to prolong the QT/QTc interval compared to several other antipsychotic drugs [see Warnings and Precautions (5.3)]. Prolongation of the QTc interval is associated in some other drugs with the ability to cause torsade de pointes-type arrhythmia, a potentially fatal polymorphic ventricular tachycardia, and sudden death. In many cases this would lead to the conclusion that other drugs should be tried first. Whether ziprasidone will cause torsade de pointes or increase the rate of sudden death is not yet known [see Warnings and Precautions (5.3)].

Schizophrenia

- GEODON is indicated for the treatment of schizophrenia in adults [see Clinical Studies (14.1)].

Bipolar I Disorder (Acute Mixed or Manic Episodes and Maintenance Treatment as an Adjunct to Lithium or Valproate)

- GEODON is indicated as monotherapy for the acute treatment of adults with manic or mixed episodes associated with bipolar I disorder [see Clinical Studies (14.2)].
- GEODON is indicated as an adjunct to lithium or valproate for the maintenance treatment of bipolar I disorder in adults [see Clinical Studies (14.2)].

Acute Treatment of Agitation in Schizophrenia

- GEODON intramuscular is indicated for the treatment of acute agitation in schizophrenic adult patients for whom treatment with ziprasidone is appropriate and who need intramuscular antipsychotic medication for rapid control of agitation [see Clinical Studies (14.1)].
  Since there is no experience regarding the safety of administering ziprasidone intramuscular to schizophrenic patients already taking oral ziprasidone, the practice of co-administration is not recommended.

2 DOSAGE AND ADMINISTRATION

2.1 Administration Information for GEODON Capsules

Administer GEODON capsules orally with food. Swallow capsules whole, do not open, crush, or chew the capsules.

2.2 Schizophrenia

Dose Selection

GEODON capsules should be administered at an initial daily dose of 20 mg twice daily with food. In some patients, daily dosage may subsequently be adjusted on the basis of individual clinical status up to 80 mg twice daily. Dosage adjustments, if indicated, should generally occur at intervals of not less than 2 days, as steady-state is achieved within 1 to 3 days. In order to ensure use of the lowest effective dose, patients should ordinarily be observed for improvement for several weeks before upward dosage adjustment.

Efficacy in schizophrenia was demonstrated in a dose range of 20 mg to 100 mg twice daily in short-term, placebo-controlled clinical trials. There were trends toward dose response within the range of 20 mg to 80 mg twice daily, but results were not consistent. An increase to a dose greater than 80 mg twice daily is not generally recommended. The safety of doses above 100 mg twice daily has not been systematically evaluated in clinical trials [see Clinical Studies (14.1)].

Maintenance Treatment

While there is no body of evidence available to answer the question of how long a patient treated with ziprasidone should remain on it, a maintenance study in patients who had been symptomatically stable and then randomized to continue ziprasidone or switch to placebo demonstrated a delay in time to relapse for patients receiving GEODON [see Clinical Studies (14.1)]. No additional benefit was demonstrated for doses above 20 mg twice daily. Patients should be periodically reassessed to determine the need for maintenance treatment.

2.3 Bipolar I Disorder (Acute Mixed or Manic Episodes and Maintenance Treatment as an Adjunct to Lithium or Valproate)

Acute Treatment of Manic or Mixed Episodes

In adults oral ziprasidone should be administered at an initial daily dose of 40 mg twice daily with food. The dose may then be increased to 60 mg or 80 mg twice daily on the second day of treatment and subsequently adjusted on the basis of tolerance and efficacy within the range 40 mg-80 mg twice daily. In the flexible-dose clinical trials, the mean daily dose administered was approximately 120 mg [see Clinical Studies (14.2)].

Maintenance Treatment (as an adjunct to lithium or valproate)

Continue treatment at the same dose on which the patient was initially stabilized, within the range of 40 mg-80 mg twice daily with food. Patients should be periodically reassessed to determine the need for maintenance treatment [see Clinical Studies (14.2)].

2.4 Acute Treatment of Agitation in Schizophrenia

Intramuscular Dosing

The recommended dose is 10 mg to 20 mg administered as required up to a maximum dose of 40 mg per day. Doses of 10 mg may be administered every two hours; doses of 20 mg may be administered every four hours up to a maximum of 40 mg/day. Intramuscular administration of ziprasidone for more than three consecutive days has not been studied.

If long-term therapy is indicated, oral ziprasidone hydrochloride capsules should replace the intramuscular administration as soon as possible.

Since there is no experience regarding the safety of administering ziprasidone intramuscular to schizophrenic patients already taking oral ziprasidone, the practice of co-administration is not recommended.

Ziprasidone intramuscular is intended for intramuscular use only and should not be administered intravenously.

Intramuscular Preparation for Administration

GEODON for Injection (ziprasidone mesylate) should only be administered by intramuscular injection and should not be administered intravenously. Single-dose vials require reconstitution prior to administration.

Add 1.2 mL of Sterile Water for Injection to the vial and shake vigorously until all the drug is dissolved. Each mL of reconstituted solution contains 20 mg ziprasidone.

To administer a 10 mg dose, draw up 0.5 mL of the reconstituted solution. To administer a 20 mg dose, draw up 1.0 mL of the reconstituted solution. Any unused portion should be discarded. Since no preservative or bacteriostatic agent is present in this product, aseptic technique must be used in preparation of the final solution. This medicinal product must not be mixed with other medicinal products or solvents other than Sterile Water for Injection. Parenteral drug products should be inspected visually for particulate matter and discoloration prior to administration, whenever solution and container permit.

2.5 Switching Patients to or from a Monoamine Oxidase Inhibitor (MAOI) Antidepressant

At least 14 days must elapse between discontinuation of an MAOI (intended to treat psychiatric disorders) and initiation of therapy with GEODON. In addition, at least 3 days should be allowed after stopping GEODON before starting an MAOI intended to treat psychiatric disorders [see Contraindications (4.3), Warnings and Precautions (5.2), and Drug Interactions (7.1)].

3 DOSAGE FORMS AND STRENGTHS

GEODON capsules are differentiated by capsule color/size and are imprinted in black ink with “Pfizer and ZDX [dosage strength]” or “Pfizer” and a unique number. GEODON capsules are supplied for oral administration in 20 mg (blue/white), 40 mg (blue/blue), 60 mg (white/white), and 80 mg (blue/white) capsules. They are supplied in the following strengths and package configurations:

GEODON Capsules | OR |  | GEODON Capsules
Capsule Strength (mg) | Imprint | Capsule Strength (mg) | Imprint
20 | ZDX 20 | 20 | 396
40 | ZDX 40 | 40 | 397
60 | ZDX 60 | 60 | 398
80 | ZDX 80 | 80 | 399

GEODON for Injection is available in a single-dose vial as ziprasidone mesylate (20 mg ziprasidone/mL when reconstituted according to label instructions) [see Dosage and Administration (2.4)]. Each mL of ziprasidone mesylate for injection (when reconstituted) affords a colorless to pale pink solution that contains 20 mg of ziprasidone and 4.7 mg of methanesulfonic acid solubilized by 294 mg of sulfobutylether β-cyclodextrin sodium (SBECD).

4 CONTRAINDICATIONS

4.1 QT Prolongation

Because of ziprasidone’s dose-related prolongation of the QT interval and the known association of fatal arrhythmias with QT prolongation by some other drugs, ziprasidone is contraindicated:

- in patients with a known history of QT prolongation (including congenital long QT syndrome)
- in patients with recent acute myocardial infarction
- in patients with uncompensated heart failure

Pharmacokinetic/pharmacodynamic studies between ziprasidone and other drugs that prolong the QT interval have not been performed. An additive effect of ziprasidone and other drugs that prolong the QT interval cannot be excluded. Therefore, ziprasidone should not be given with:

- dofetilide, sotalol, quinidine, other Class Ia and III anti-arrhythmics, mesoridazine, thioridazine, chlorpromazine, droperidol, pimozide, sparfloxacin, gatifloxacin, moxifloxacin, halofantrine, mefloquine, pentamidine, arsenic trioxide, levomethadyl acetate, dolasetron mesylate, probucol or tacrolimus.
- other drugs that have demonstrated QT prolongation as one of their pharmacodynamic effects and have this effect described in the full prescribing information as a contraindication or a boxed or bolded warning [see Warnings and Precautions (5.3)].

4.2 Hypersensitivity

Ziprasidone is contraindicated in individuals with a known hypersensitivity to the product.

4.3 Monoamine Oxidase Inhibitors (MAOIs)

Ziprasidone is contraindicated in patients taking, or within 14 days of stopping, MAOIs (including the MAOIs linezolid and intravenous methylene blue) because of an increased risk of serotonin syndrome [see Warnings and Precautions (5.4), Drug Interaction (7.3)].

5 WARNINGS AND PRECAUTIONS

5.1 Increased Mortality in Elderly Patients with Dementia-Related Psychosis

Elderly patients with dementia-related psychosis treated with antipsychotic drugs are at an increased risk of death. Analyses of 17 placebo-controlled trials (modal duration of 10 weeks), largely in patients taking atypical antipsychotic drugs, revealed a risk of death in drug-treated patients of between 1.6 to 1.7 times the risk of death in placebo-treated patients. Over the course of a typical 10-week controlled trial, the rate of death in drug-treated patients was about 4.5%, compared to a rate of about 2.6% in the placebo group.

Although the causes of death were varied, most of the deaths appeared to be either cardiovascular (e.g., heart failure, sudden death) or infectious (e.g., pneumonia) in nature. GEODON is not approved for the treatment of patients with dementia-related psychosis. [see Boxed Warning, Warnings and Precautions (5.2)].

5.2 Cerebrovascular Adverse Reactions, Including Stroke, in Elderly Patients with Dementia-Related Psychosis

In placebo-controlled trials in elderly subjects with dementia, patients randomized to risperidone, aripiprazole, and olanzapine had a higher incidence of stroke and transient ischemic attack, including fatal stroke. GEODON is not approved for the treatment of patients with dementia-related psychosis [see Boxed Warning and Warnings and Precautions (5.1)].

5.3 QT Prolongation and Risk of Sudden Death

Ziprasidone use should be avoided in combination with other drugs that are known to prolong the QTc interval [see Contraindications (4.1) and Drug Interactions (7.4)]. Additionally, clinicians should be alert to the identification of other drugs that have been consistently observed to prolong the QTc interval. Such drugs should not be prescribed with ziprasidone. Ziprasidone should also be avoided in patients with congenital long QT syndrome and in patients with a history of cardiac arrhythmias [see Contraindications (4)].

A study directly comparing the QT/QTc prolonging effect of oral ziprasidone with several other drugs effective in the treatment of schizophrenia was conducted in patient volunteers. In the first phase of the trial, ECGs were obtained at the time of maximum plasma concentration when the drug was administered alone. In the second phase of the trial, ECGs were obtained at the time of maximum plasma concentration while the drug was co-administered with an inhibitor of the CYP4503A4 metabolism of the drug.

In the first phase of the study, the mean change in QTc from baseline was calculated for each drug, using a sample-based correction that removes the effect of heart rate on the QT interval. The mean increase in QTc from baseline for ziprasidone ranged from approximately 9 to 14 msec greater than for four of the comparator drugs (risperidone, olanzapine, quetiapine, and haloperidol), but was approximately 14 msec less than the prolongation observed for thioridazine.

In the second phase of the study, the effect of ziprasidone on QTc length was not augmented by the presence of a metabolic inhibitor (ketoconazole 200 mg twice daily).

In placebo-controlled trials in adults, oral ziprasidone increased the QTc interval compared to placebo by approximately 10 msec at the highest recommended daily dose of 160 mg. In clinical trials with oral ziprasidone, the electrocardiograms of 2/2988 (0.06%) patients who received GEODON and 1/440 (0.23%) patients who received placebo revealed QTc intervals exceeding the potentially clinically relevant threshold of 500 msec. In the ziprasidone-treated patients, neither case suggested a role of ziprasidone. One patient had a history of prolonged QTc and a screening measurement of 489 msec; QTc was 503 msec during ziprasidone treatment. The other patient had a QTc of 391 msec at the end of treatment with ziprasidone and upon switching to thioridazine experienced QTc measurements of 518 and 593 msec.

Some drugs that prolong the QT/QTc interval have been associated with the occurrence of torsade de pointes and with sudden unexplained death. The relationship of QT prolongation to torsade de pointes is clearest for larger increases (20 msec and greater) but it is possible that smaller QT/QTc prolongations may also increase risk, or increase it in susceptible individuals. Although torsade de pointes has not been observed in association with the use of ziprasidone in premarketing studies and experience is too limited to rule out an increased risk, there have been rare post-marketing reports (in the presence of multiple confounding factors) [see Adverse Reactions (6.2)].

A study evaluating the QT/QTc prolonging effect of intramuscular ziprasidone, with intramuscular haloperidol as a control, was conducted in patient volunteers. In the trial, ECGs were obtained at the time of maximum plasma concentration following two injections of ziprasidone (20 mg then 30 mg) or haloperidol (7.5 mg then 10 mg) given four hours apart. Note that a 30 mg dose of intramuscular ziprasidone is 50% higher than the recommended therapeutic dose. The mean change in QTc from baseline was calculated for each drug, using a sample-based correction that removes the effect of heart rate on the QT interval. The mean increase in QTc from baseline for ziprasidone was 4.6 msec following the first injection and 12.8 msec following the second injection. The mean increase in QTc from baseline for haloperidol was 6.0 msec following the first injection and 14.7 msec following the second injection. In this study, no patients had a QTc interval exceeding 500 msec.

As with other antipsychotic drugs and placebo, sudden unexplained deaths have been reported in patients taking ziprasidone at recommended doses. The premarketing experience for ziprasidone did not reveal an excess risk of mortality for ziprasidone compared to other antipsychotic drugs or placebo, but the extent of exposure was limited, especially for the drugs used as active controls and placebo. Nevertheless, ziprasidone’s larger prolongation of QTc length compared to several other antipsychotic drugs raises the possibility that the risk of sudden death may be greater for ziprasidone than for other available drugs for treating schizophrenia. This possibility needs to be considered in deciding among alternative drug products [see Indications and Usage (1)].

Certain circumstances may increase the risk of the occurrence of torsade de pointes and/or sudden death in association with the use of drugs that prolong the QTc interval, including (1) bradycardia; (2) hypokalemia or hypomagnesemia; (3) concomitant use of other drugs that prolong the QTc interval; and (4) presence of congenital prolongation of the QT interval.

It is recommended that patients being considered for ziprasidone treatment who are at risk for significant electrolyte disturbances, hypokalemia in particular, have baseline serum potassium and magnesium measurements. Hypokalemia (and/or hypomagnesemia) may increase the risk of QT prolongation and arrhythmia. Hypokalemia may result from diuretic therapy, diarrhea, and other causes. Patients with low serum potassium and/or magnesium should be repleted with those electrolytes before proceeding with treatment. It is essential to periodically monitor serum electrolytes in patients for whom diuretic therapy is introduced during ziprasidone treatment. Persistently prolonged QTc intervals may also increase the risk of further prolongation and arrhythmia, but it is not clear that routine screening ECG measures are effective in detecting such patients. Rather, ziprasidone should be avoided in patients with histories of significant cardiovascular illness, e.g., QT prolongation, recent acute myocardial infarction, uncompensated heart failure, or cardiac arrhythmia. Ziprasidone should be discontinued in patients who are found to have persistent QTc measurements >500 msec.

For patients taking ziprasidone who experience symptoms that could indicate the occurrence of torsade de pointes, e.g., dizziness, palpitations, or syncope, the prescriber should initiate further evaluation, e.g., Holter monitoring may be useful.

5.4 Serotonin Syndrome

Ziprasidone can precipitate serotonin syndrome, a potentially life-threatening condition. The risk is increased with concomitant use of other serotonergic drugs (including selective serotonin reuptake inhibitors (SSRIs), serotonin norepinephrine reuptake inhibitors (SNRIs), triptans, tricyclic antidepressants, fentanyl, tramadol, meperidine, methadone, lithium, tryptophan, buspirone, amphetamines, and St. John’s Wort) and with drugs that impair metabolism of serotonin, i.e., monoamine oxidase inhibitors (MAOIs) [see Contraindications (4.3), Adverse Reactions (6.2), Drug Interactions (7.3)].

Serotonin syndrome signs and symptoms may include mental status changes (e.g., agitation, hallucinations, delirium, and coma), autonomic instability (e.g., tachycardia, labile blood pressure, dizziness, diaphoresis, flushing, hyperthermia), neuromuscular symptoms (e.g., tremor, rigidity, myoclonus, hyperreflexia, incoordination), seizures, and gastrointestinal symptoms (e.g., nausea, vomiting, diarrhea).

The concomitant use of GEODON with MAOIs is contraindicated. In addition, do not initiate GEODON in a patient being treated with MAOIs such as linezolid or intravenous methylene blue. If it is necessary to initiate treatment with an MAOI such as linezolid or intravenous methylene blue in a patient taking GEODON, discontinue GEODON before initiating treatment with the MAOI [see Contraindications (4.3), Drug Interactions (7.3)].

Monitor all patients taking GEODON for the emergence of serotonin syndrome. Discontinue treatment with GEODON and any concomitant serotonergic agents immediately if the above symptoms occur, and initiate supportive symptomatic treatment. If concomitant use of GEODON with other serotonergic drugs is clinically warranted, inform patients of the increased risk of serotonin syndrome and monitor for symptoms.

5.5 Neuroleptic Malignant Syndrome (NMS)

A potentially fatal symptom complex sometimes referred to as Neuroleptic Malignant Syndrome (NMS) has been reported in association with administration of antipsychotic drugs. Clinical manifestations of NMS are hyperpyrexia, muscle rigidity, altered mental status, and evidence of autonomic instability (irregular pulse or blood pressure, tachycardia, diaphoresis, and cardiac dysrhythmia). Additional signs may include elevated creatinine phosphokinase, myoglobinuria (rhabdomyolysis), and acute renal failure.

The diagnostic evaluation of patients with this syndrome is complicated. In arriving at a diagnosis, it is important to exclude cases where the clinical presentation includes both serious medical illness (e.g., pneumonia, systemic infection, etc.) and untreated or inadequately treated extrapyramidal signs and symptoms (EPS). Other important considerations in the differential diagnosis include central anticholinergic toxicity, heat stroke, drug fever, and primary central nervous system (CNS) pathology.

The management of NMS should include: (1) immediate discontinuation of antipsychotic drugs and other drugs not essential to concurrent therapy; (2) intensive symptomatic treatment and medical monitoring; and (3) treatment of any concomitant serious medical problems for which specific treatments are available. There is no general agreement about specific pharmacological treatment regimens for NMS.

If a patient requires antipsychotic drug treatment after recovery from NMS, the potential reintroduction of drug therapy should be carefully considered. The patient should be carefully monitored, since recurrences of NMS have been reported.

5.6 Severe Cutaneous Adverse Reactions

Drug Reaction with Eosinophilia and Systemic Symptoms (DRESS) has been reported with Ziprasidone exposure. DRESS consists of a combination of three or more of the following: cutaneous reaction (such as rash or exfoliative dermatitis), eosinophilia, fever, lymphadenopathy and one or more systemic complications such as hepatitis, nephritis, pneumonitis, myocarditis, and pericarditis. DRESS is sometimes fatal. Discontinue ziprasidone if DRESS is suspected.

Other severe cutaneous adverse reactions, such as Stevens-Johnson syndrome, have been reported with ziprasidone exposure. Severe cutaneous adverse reactions are sometimes fatal. Discontinue ziprasidone if severe cutaneous adverse reactions are suspected.

5.7 Tardive Dyskinesia

A syndrome of potentially irreversible, involuntary, dyskinetic movements may develop in patients undergoing treatment with antipsychotic drugs. Although the prevalence of the syndrome appears to be highest among the elderly, especially elderly women, it is impossible to rely upon prevalence estimates to predict, at the inception of antipsychotic treatment, which patients are likely to develop the syndrome. Whether antipsychotic drug products differ in their potential to cause tardive dyskinesia is unknown.

The risk of developing tardive dyskinesia and the likelihood that it will become irreversible are believed to increase as the duration of treatment and the total cumulative dose of antipsychotic drugs administered to the patient increase. However, the syndrome can develop, although much less commonly, after relatively brief treatment periods at low doses.

There is no known treatment for established cases of tardive dyskinesia, although the syndrome may remit, partially or completely, if antipsychotic treatment is withdrawn. Antipsychotic treatment itself, however, may suppress (or partially suppress) the signs and symptoms of the syndrome, and thereby may possibly mask the underlying process. The effect that symptomatic suppression has upon the long-term course of the syndrome is unknown.

Given these considerations, ziprasidone should be prescribed in a manner that is most likely to minimize the occurrence of tardive dyskinesia. Chronic antipsychotic treatment should generally be reserved for patients who suffer from a chronic illness that (1) is known to respond to antipsychotic drugs, and (2) for whom alternative, equally effective, but potentially less harmful treatments are not available or appropriate. In patients who do require chronic treatment, the smallest dose and the shortest duration of treatment producing a satisfactory clinical response should be sought. The need for continued treatment should be reassessed periodically.

If signs and symptoms of tardive dyskinesia appear in a patient on ziprasidone, drug discontinuation should be considered. However, some patients may require treatment with ziprasidone despite the presence of the syndrome.

5.8 Metabolic Changes

Atypical antipsychotic drugs have been associated with metabolic changes that may increase cardiovascular/cerebrovascular risk. These metabolic changes include hyperglycemia, dyslipidemia, and body weight gain. While all of the drugs in the class have been shown to produce some metabolic changes, each drug has its own specific risk profile.

Hyperglycemia and diabetes mellitus, in some cases extreme and associated with ketoacidosis or hyperosmolar coma or death, have been reported in patients treated with atypical antipsychotics. There have been few reports of hyperglycemia or diabetes in patients treated with GEODON. Although fewer patients have been treated with GEODON, it is not known if this more limited experience is the sole reason for the paucity of such reports. Assessment of the relationship between atypical antipsychotic use and glucose abnormalities is complicated by the possibility of an increased background risk of diabetes mellitus in patients with schizophrenia and the increasing incidence of diabetes mellitus in the general population. Given these confounders, the relationship between atypical antipsychotic use and hyperglycemia-related adverse reactions is not completely understood. Precise risk estimates for hyperglycemia-related adverse reactions in patients treated with atypical antipsychotics are not available.

Patients with an established diagnosis of diabetes mellitus who are started on atypical antipsychotics should be monitored regularly for worsening of glucose control. Patients with risk factors for diabetes mellitus (e.g., obesity, family history of diabetes) who are starting treatment with atypical antipsychotics should undergo fasting blood glucose testing at the beginning of treatment and periodically during treatment. Any patient treated with atypical antipsychotics should be monitored for symptoms of hyperglycemia including polydipsia, polyuria, polyphagia, and weakness. Patients who develop symptoms of hyperglycemia during treatment with atypical antipsychotics should undergo fasting blood glucose testing. In some cases, hyperglycemia has resolved when the atypical antipsychotic was discontinued; however, some patients required continuation of antidiabetic treatment despite discontinuation of the suspect drug.

Pooled data from short-term, placebo-controlled studies in schizophrenia and bipolar disorder are presented in Tables 1-4. Note that for the flexible dose studies in both schizophrenia and bipolar disorder, each subject is categorized as having received either low (20-40 mg BID) or high (60-80 mg BID) dose based on the subject’s modal daily dose. In the tables showing categorical changes, the percentages (% column) are calculated as 100x(n/N).

Table 1: Glucose [“Random” glucose measurements—fasting/non-fasting status unknown] Mean Change from Baseline in Short-Term (up to 6 weeks), Placebo-Controlled, Fixed-Dose, Oral Ziprasidone, Monotherapy Trials in Adult Patients with Schizophrenia
Mean Random Glucose Change from Baseline mg/dL (N)
Ziprasidone |  |  |  |  |  | Placebo
5 mg BID | 20 mg BID | 40 mg BID | 60 mg BID | 80 mg BID | 100 mg BID | Placebo
-1.1 (N=45) | +2.4 (N=179) | -0.2 (N=146) | -0.5 (N=119) | -1.7 (N=104) | +4.1 (N=85) | +1.4 (N=260)

Table 2: Glucose [“Random” glucose measurements – fasting/non-fasting status unknown] Categorical Changes in Short-Term (up to 6 weeks), Placebo-Controlled, Fixed-Dose, Oral Ziprasidone, Monotherapy Trials in Adult Patients with Schizophrenia
Laboratory Analyte | Category Change (at least once) from Baseline | Treatment Arm | N | n (%)
Random Glucose | Normal to High (<100 mg/dL to ≥126 mg/dL) | Ziprasidone | 438 | 77 (17.6%)
Random Glucose | Normal to High (<100 mg/dL to ≥126 mg/dL) | Placebo | 169 | 26 (15.4%)
Random Glucose | Borderline to High (≥100 mg/dL and <126 mg/dL to ≥126 mg/dL) | Ziprasidone | 159 | 54 (34.0%)
Random Glucose | Borderline to High (≥100 mg/dL and <126 mg/dL to ≥126 mg/dL) | Placebo | 66 | 22 (33.3%)

In long-term (at least 1 year), placebo-controlled, flexible-dose studies in schizophrenia, the mean change from baseline in random glucose for ziprasidone 20-40 mg BID was -3.4 mg/dL (N=122); for ziprasidone 60-80 mg BID was +1.3 mg/dL (N=10); and for placebo was +0.3 mg/dL (N=71).

Table 3: Glucose [Fasting] Mean Change from Baseline in Short-Term (up to 6 weeks), Placebo-Controlled, Flexible-Dose, Oral Ziprasidone, Monotherapy Trials in Adult Patients with Bipolar Disorder
Mean Fasting Glucose Change from Baseline mg/dL (N)
Ziprasidone |  | Placebo
Low Dose: 20-40 mg BID | High Dose: 60-80 mg BID | Placebo
+0.1 (N=206) | +1.6 (N=166) | +1.4 (N=287)

Table 4: Glucose [Fasting] Categorical Changes in Short-Term (up to 6 weeks), Placebo-Controlled, Flexible-Dose, Oral Ziprasidone, Monotherapy Trials in Adult Patients with Bipolar Disorder
Laboratory Analyte | Category Change (at least once) from Baseline | Treatment Arm | N | n (%)
Fasting Glucose | Normal to High (<100 mg/dL to ≥126 mg/dL) | Ziprasidone | 272 | 5 (1.8%)
Fasting Glucose | Normal to High (<100 mg/dL to ≥126 mg/dL) | Placebo | 210 | 2 (1.0%)
Fasting Glucose | Borderline to High (≥100 mg/dL and <126 mg/dL to ≥126 mg/dL) | Ziprasidone | 79 | 12 (15.2%)
Fasting Glucose | Borderline to High (≥100 mg/dL and <126 mg/dL to ≥126 mg/dL) | Placebo | 71 | 7 (9.9%)

Dyslipidemia

Undesirable alterations in lipids have been observed in patients treated with atypical antipsychotics. Pooled data from short-term, placebo-controlled studies in schizophrenia and bipolar disorder are presented in Tables 5-8.

Table 5: Lipid [“Random” lipid measurements, fasting/non-fasting status unknown] Mean Change from Baseline in Short-Term (up to 6 weeks), Placebo-Controlled, Fixed-Dose, Oral Ziprasidone, Monotherapy Trials in Adult Patients with Schizophrenia
Mean Lipid Change from Baseline mg/dL (N)
Laboratory Analyte | Ziprasidone |  |  |  |  |  | Placebo
Laboratory Analyte | 5 mg BID | 20 mg BID | 40 mg BID | 60 mg BID | 80 mg BID | 100 mg BID | Placebo
Triglycerides | -12.9 (N=45) | -9.6 (N=181) | -17.3 (N=146) | -0.05 (N=120) | -16.0 (N=104) | +0.8 (N=85) | -18.6 (N=260)
Total Cholesterol | -3.6 (N=45) | -4.4 (N=181) | -8.2 (N=147) | -3.6 (N=120) | -10.0 (N=104) | -3.6 (N=85) | -4.7 (N=261)

Table 6: Lipid [“Random” lipid measurements, fasting/non-fasting status unknown] Categorical Changes in Short-Term (up to 6 weeks), Placebo-Controlled, Fixed-Dose, Oral Ziprasidone, Monotherapy Trials in Adult Patients with Schizophrenia
Laboratory Analyte | Category Change (at least once) from Baseline | Treatment Arm | N | n (%)
Triglycerides | Increase by ≥50 mg/dL | Ziprasidone | 681 | 232 (34.1%)
Triglycerides | Increase by ≥50 mg/dL | Placebo | 260 | 53 (20.4%)
Triglycerides | Normal to High (<150 mg/dL to ≥200 mg/dL) | Ziprasidone | 429 | 63 (14.7%)
Triglycerides | Normal to High (<150 mg/dL to ≥200 mg/dL) | Placebo | 152 | 12 (7.9%)
Triglycerides | Borderline to High (≥150 mg/dL and <200 mg/dL to ≥200 mg/dL) | Ziprasidone | 92 | 43 (46.7%)
Triglycerides | Borderline to High (≥150 mg/dL and <200 mg/dL to ≥200 mg/dL) | Placebo | 41 | 12 (29.3%)
Total Cholesterol | Increase by ≥40 mg/dL | Ziprasidone | 682 | 76 (11.1%)
Total Cholesterol | Increase by ≥40 mg/dL | Placebo | 261 | 26 (10.0%)
Total Cholesterol | Normal to High (<200 mg/dL to ≥240 mg/dL) | Ziprasidone | 380 | 15 (3.9%)
Total Cholesterol | Normal to High (<200 mg/dL to ≥240 mg/dL) | Placebo | 145 | 0 (0.0%)
Total Cholesterol | Borderline to High (≥200 mg/dL and <240 mg/dL to ≥240 mg/dL) | Ziprasidone | 207 | 56 (27.1%)
Total Cholesterol | Borderline to High (≥200 mg/dL and <240 mg/dL to ≥240 mg/dL) | Placebo | 82 | 22 (26.8%)

In long-term (at least 1 year), placebo-controlled, flexible-dose studies in schizophrenia, the mean change from baseline in random triglycerides for ziprasidone 20-40 mg BID was +26.3 mg/dL (N=15); for ziprasidone 60-80 mg BID was -39.3 mg/dL (N=10); and for placebo was +12.9 mg/dL (N=9). In long-term (at least 1 year), placebo-controlled, flexible-dose studies in schizophrenia, the mean change from baseline in random total cholesterol for ziprasidone 20-40 mg BID was +2.5 mg/dL (N=14); for ziprasidone 60-80 mg BID was -19.7 mg/dL (N=10); and for placebo was -28.0 mg/dL (N=9).

Table 7: Lipid [Fasting] Mean Change from Baseline in Short-Term (up to 6 weeks), Placebo-Controlled, Flexible-Dose, Oral Ziprasidone, Monotherapy Trials in Adult Patients with Bipolar Disorder
Laboratory Analyte | Mean Change from Baseline mg/dL (N)
Laboratory Analyte | Ziprasidone |  | Placebo
Laboratory Analyte | Low Dose: 20-40 mg BID | High Dose: 60-80 mg BID | Placebo
Fasting Triglycerides | +0.95 (N=206) | -3.5 (N=165) | +8.6 (N=286)
Fasting Total Cholesterol | -2.8 (N=206) | -3.4 (N=165) | -1.6 (N=286)
Fasting LDL Cholesterol | -3.0 (N=201) | -3.1 (N=158) | -1.97 (N=270)
Fasting HDL Cholesterol | -0.09 (N=206) | +0.3 (N=165) | -0.9 (N=286)

Table 8: Lipid [Fasting] Categorical Changes in Short-Term (up to 6 weeks), Placebo-Controlled, Flexible-Dose, Oral Ziprasidone, Monotherapy Trials in Adult Patients with Bipolar Disorder
Laboratory Analyte | Category Change (at least once) from Baseline | Treatment Arm | N | n (%)
Fasting Triglycerides | Increase by ≥50 mg/dL | Ziprasidone | 371 | 66 (17.8%)
Fasting Triglycerides | Increase by ≥50 mg/dL | Placebo | 286 | 62 (21.7%)
Fasting Triglycerides | Normal to High (<150 mg/dL to ≥200 mg/dL) | Ziprasidone | 225 | 15 (6.7%)
Fasting Triglycerides | Normal to High (<150 mg/dL to ≥200 mg/dL) | Placebo | 179 | 13 (7.3%)
Fasting Triglycerides | Borderline to High (≥150 mg/dL and <200 mg/dL to ≥200 mg/dL) | Ziprasidone | 58 | 16 (27.6%)
Fasting Triglycerides | Borderline to High (≥150 mg/dL and <200 mg/dL to ≥200 mg/dL) | Placebo | 47 | 14 (29.8%)
Fasting Total Cholesterol | Increase by ≥40 mg/dL | Ziprasidone | 371 | 30 (8.1%)
Fasting Total Cholesterol | Increase by ≥40 mg/dL | Placebo | 286 | 13 (4.5%)
Fasting Total Cholesterol | Normal to High (<200 mg/dL to ≥240 mg/dL) | Ziprasidone | 204 | 5 (2.5%)
Fasting Total Cholesterol | Normal to High (<200 mg/dL to ≥240 mg/dL) | Placebo | 151 | 2 (1.3%)
Fasting Total Cholesterol | Borderline to High (≥200 mg/dL and <240 mg/dL to ≥240 mg/dL) | Ziprasidone | 106 | 10 (9.4%)
Fasting Total Cholesterol | Borderline to High (≥200 mg/dL and <240 mg/dL to ≥240 mg/dL) | Placebo | 87 | 15 (17.2%)
Fasting LDL Cholesterol | Increase by ≥30 mg/dL | Ziprasidone | 359 | 39 (10.9%)
Fasting LDL Cholesterol | Increase by ≥30 mg/dL | Placebo | 270 | 17 (6.3%)
Fasting LDL Cholesterol | Normal to High (<100 mg/dL to ≥160 mg/dL) | Ziprasidone | 115 | 0 (0%)
Fasting LDL Cholesterol | Normal to High (<100 mg/dL to ≥160 mg/dL) | Placebo | 89 | 1 (1.1%)
Fasting LDL Cholesterol | Borderline to High (≥100 mg/dL and <160 mg/dL to ≥160 mg/dL) | Ziprasidone | 193 | 18 (9.3%)
Fasting LDL Cholesterol | Borderline to High (≥100 mg/dL and <160 mg/dL to ≥160 mg/dL) | Placebo | 141 | 14 (9.9%)
Fasting HDL | Normal (>=40 mg/dL) to Low (<40 mg/dL) | Ziprasidone | 283 | 22 (7.8%)
Fasting HDL | Normal (>=40 mg/dL) to Low (<40 mg/dL) | Placebo | 220 | 24 (10.9%)

Weight Gain

Weight gain has been observed with atypical antipsychotic use. Monitoring of weight is recommended. Pooled data from short-term, placebo-controlled studies in schizophrenia and bipolar disorder are presented in Tables 9-10.

Table 9: Weight Mean Changes in Short-Term (up to 6 weeks), Placebo-Controlled, Fixed-Dose, Oral Ziprasidone, Monotherapy Trials in Adult Patients with Schizophrenia
Ziprasidone |  |  |  |  |  | Placebo
5 mg BID | 20 mg BID | 40 mg BID | 60 mg BID | 80 mg BID | 100 mg BID | Placebo
Mean Weight (kg) Changes from Baseline (N)
+0.3 (N=40) | +1.0 (N=167) | +1.0 (N=135) | +0.7 (N=109) | +1.1 (N=97) | +0.9 (N=74) | -0.4 (227)
Proportion of Patients with ≥7% Increase in Weight from Baseline (N)
0.0% (N=40) | 9.0% (N=167) | 10.4% (N=135) | 7.3% (N=109) | 15.5% (N=97) | 10.8% (N=74) | 4.0% (N=227)

In long-term (at least 1 year), placebo-controlled, flexible-dose studies in schizophrenia, the mean change from baseline weight for ziprasidone 20-40 mg BID was -2.3 kg (N=124); for ziprasidone 60-80 mg BID was +2.5 kg (N=10); and for placebo was -2.9 kg (N=72). In the same long-term studies, the proportion of subjects with ≥7% increase in weight from baseline for ziprasidone 20-40 mg BID was 5.6% (N=124); for ziprasidone 60-80 mg BID was 20.0% (N=10), and for placebo was 5.6% (N=72). In a long-term (at least 1 year), placebo-controlled, fixed-dose study in schizophrenia, the mean change from baseline weight for ziprasidone 20 mg BID was -2.6 kg (N=72); for ziprasidone 40 mg BID was -3.3 kg (N=69); for ziprasidone 80 mg BID was -2.8 kg (N=70) and for placebo was -3.8 kg (N=70). In the same long-term fixed-dose schizophrenia study, the proportion of subjects with ≥7% increase in weight from baseline for ziprasidone 20 mg BID was 5.6% (N=72); for ziprasidone 40 mg BID was 2.9% (N=69); for ziprasidone 80 mg BID was 5.7% (N=70) and for placebo was 2.9% (N=70).

Table 10: Summary of Weight Change in Short-Term (up to 6 weeks), Placebo-Controlled, Flexible-Dose, Oral Ziprasidone, Monotherapy Trials in Adult Patients with Bipolar Disorder
Ziprasidone |  | Placebo
Low Dose: 20-40 mg BID | High Dose [Note that in the High Dose group, there were 2 subjects with modal 200 mg total daily dose and 1 subject with modal 100 mg total daily dose.] : 60-80 mg BID | Placebo
Mean Weight (kg) Changes from Baseline (N)
+0.4 (N=295) | +0.4 (N=388) | +0.1 (N=451)
Proportion of Patients with ≥7% Increase in Weight from Baseline (N)
2.4% (N=295) | 4.4% (N=388) | 1.8% (N=451)

Schizophrenia

The proportions of patients meeting a weight gain criterion of ≥7% of body weight were compared in a pool of four 4- and 6-week placebo-controlled schizophrenia clinical trials, revealing a statistically significantly greater incidence of weight gain for ziprasidone (10%) compared to placebo (4%). A median weight gain of 0.5 kg was observed in ziprasidone patients compared to no median weight change in placebo patients. In this set of clinical trials, weight gain was reported as an adverse reaction in 0.4% and 0.4% of ziprasidone and placebo patients, respectively. During long-term therapy with ziprasidone, a categorization of patients at baseline on the basis of body mass index (BMI) revealed the greatest mean weight gain and highest incidence of clinically significant weight gain (> 7% of body weight) in patients with low BMI (<23) compared to normal (23-27) or overweight patients (>27). There was a mean weight gain of 1.4 kg for those patients with a “low” baseline BMI, no mean change for patients with a “normal” BMI, and a 1.3 kg mean weight loss for patients who entered the program with a “high” BMI.

Bipolar Disorder

During a 6-month placebo-controlled bipolar maintenance study in adults with ziprasidone as an adjunct to lithium or valproate, the incidence of clinically significant weight gain (≥7% of body weight) during the double-blind period was 5.6% for both ziprasidone and placebo treatment groups who completed the 6 months of observation for relapse. Interpretation of these findings should take into consideration that only patients who adequately tolerated ziprasidone entered the double-blind phase of the study, and there were substantial dropouts during the open label phase.

5.9 Rash

In premarketing trials with ziprasidone, about 5% of patients developed rash and/or urticaria, with discontinuation of treatment in about one-sixth of these cases. The occurrence of rash was related to dose of ziprasidone, although the finding might also be explained by the longer exposure time in the higher dose patients. Several patients with rash had signs and symptoms of associated systemic illness, e.g., elevated WBCs. Most patients improved promptly with adjunctive treatment with antihistamines or steroids and/or upon discontinuation of ziprasidone, and all patients experiencing these reactions were reported to recover completely. Upon appearance of rash for which an alternative etiology cannot be identified, ziprasidone should be discontinued.

5.10 Orthostatic Hypotension

Ziprasidone may induce orthostatic hypotension associated with dizziness, tachycardia, and, in some patients, syncope, especially during the initial dose-titration period, probably reflecting its α1-adrenergic antagonist properties. Syncope was reported in 0.6% of the patients treated with ziprasidone.

Ziprasidone should be used with particular caution in patients with known cardiovascular disease (history of myocardial infarction or ischemic heart disease, heart failure or conduction abnormalities), cerebrovascular disease, or conditions which would predispose patients to hypotension (dehydration, hypovolemia, and treatment with antihypertensive medications).

5.11 Falls

Antipsychotic drugs (which include GEODON) may cause somnolence, postural hypotension, and motor and sensory instability, which could lead to falls and, consequently, fractures or other injuries. For patients with diseases, conditions, or medications that could exacerbate these effects, complete fall risk assessments when initiating antipsychotic treatment and recurrently for patients on long-term antipsychotic therapy.

5.12 Leukopenia, Neutropenia, and Agranulocytosis

In clinical trial and postmarketing experience, events of leukopenia/neutropenia have been reported temporally related to antipsychotic agents. Agranulocytosis (including fatal cases) has also been reported.

Possible risk factors for leukopenia/neutropenia include pre-existing low white blood cell count (WBC) and history of drug induced leukopenia/neutropenia. Patients with a pre-existing low WBC or a history of drug induced leukopenia/neutropenia should have their complete blood count (CBC) monitored frequently during the first few months of therapy and should discontinue GEODON at the first sign of decline in WBC in the absence of other causative factors.

Patients with neutropenia should be carefully monitored for fever or other symptoms or signs of infection and treated promptly if such symptoms or signs occur. Patients with severe neutropenia (absolute neutrophil count <1000/mm3) should discontinue GEODON and have their WBC followed until recovery.

5.13 Seizures

During clinical trials, seizures occurred in 0.4% of patients treated with ziprasidone. There were confounding factors that may have contributed to the occurrence of seizures in many of these cases. As with other antipsychotic drugs, ziprasidone should be used cautiously in patients with a history of seizures or with conditions that potentially lower the seizure threshold, e.g., Alzheimer’s dementia. Conditions that lower the seizure threshold may be more prevalent in a population of 65 years or older.

5.14 Dysphagia

Esophageal dysmotility and aspiration have been associated with antipsychotic drug use. Aspiration pneumonia is a common cause of morbidity and mortality in elderly patients, in particular those with advanced Alzheimer’s dementia. Ziprasidone and other antipsychotic drugs should be used cautiously in patients at risk for aspiration pneumonia [see Boxed Warning].

5.15 Hyperprolactinemia

As with other drugs that antagonize dopamine D2 receptors, ziprasidone elevates prolactin levels in humans. Increased prolactin levels were also observed in animal studies with this compound, and were associated with an increase in mammary gland neoplasia in mice; a similar effect was not observed in rats [see Nonclinical Toxicology (13.1)]. Tissue culture experiments indicate that approximately one-third of human breast cancers are prolactin-dependent in vitro, a factor of potential importance if the prescription of these drugs is contemplated in a patient with previously detected breast cancer. Published epidemiologic studies have shown inconsistent results when exploring the potential association between hyperprolactinemia and breast cancer.

Although disturbances such as galactorrhea, amenorrhea, gynecomastia, and impotence have been reported with prolactin-elevating compounds, the clinical significance of elevated serum prolactin levels is unknown for most patients. Long-standing hyperprolactinemia when associated with hypogonadism may lead to decreased bone density.

5.16 Potential for Cognitive and Motor Impairment

Somnolence was a commonly reported adverse reaction in patients treated with ziprasidone. In the 4- and 6-week placebo-controlled trials in adults, somnolence was reported in 14% of patients on ziprasidone compared to 7% of placebo patients. Somnolence led to discontinuation in 0.3% of the patients in short-term clinical trials in adults.

Since ziprasidone has the potential to impair judgment, thinking, or motor skills, patients should be cautioned about performing activities requiring mental alertness, such as operating a motor vehicle (including automobiles) or operating hazardous machinery until they are reasonably certain that ziprasidone therapy does not affect them adversely.

5.17 Priapism

One case of priapism was reported in the premarketing database. While the relationship of the reaction to ziprasidone use has not been established, other drugs with alpha-adrenergic blocking effects have been reported to induce priapism, and it is possible that ziprasidone may share this capacity. Severe priapism may require surgical intervention.

5.18 Body Temperature Regulation

Although not reported with ziprasidone in premarketing trials, disruption of the body’s ability to reduce core body temperature has been attributed to antipsychotic agents. Appropriate care is advised when prescribing ziprasidone for patients who will be experiencing conditions which may contribute to an elevation in core body temperature, e.g., exercising strenuously, exposure to extreme heat, receiving concomitant medication with anticholinergic activity, or being subject to dehydration.

5.19 Suicide

The possibility of a suicide attempt is inherent in psychotic illness or bipolar disorder, and close supervision of high-risk patients should accompany drug therapy. Prescriptions for ziprasidone should be written for the smallest quantity of capsules consistent with good patient management in order to reduce the risk of overdose.

5.20 Patients with Concomitant Illnesses

Clinical experience with ziprasidone in patients with certain concomitant systemic illnesses is limited [see Use in Specific Populations (8.6), (8.7)].

Ziprasidone has not been evaluated or used to any appreciable extent in patients with a recent history of myocardial infarction or unstable heart disease. Patients with these diagnoses were excluded from premarketing clinical studies. Because of the risk of QTc prolongation and orthostatic hypotension with ziprasidone, caution should be observed in cardiac patients. [see Warnings and Precautions (5.3), (5.10)].

5.21 Laboratory Tests

Patients being considered for ziprasidone treatment that are at risk of significant electrolyte disturbances should have baseline serum potassium and magnesium measurements. Low serum potassium and magnesium should be replaced before proceeding with treatment. Patients who are started on diuretics during Ziprasidone therapy need periodic monitoring of serum potassium and magnesium. Ziprasidone should be discontinued in patients who are found to have persistent QTc measurements >500 msec [see Warnings and Precautions (5.3)].

6 ADVERSE REACTIONS

The following adverse reactions are described in more detail in other sections of the prescribing information:

- Increased Mortality in Elderly Patients with Dementia-Related Psychosis [see Boxed Warning and Warnings and Precautions (5.1)]
- Cerebrovascular Adverse Reactions, Including Stroke, in Elderly Patients with Dementia-Related Psychosis [see Warnings and Precautions (5.2)]
- QT Prolongation and Risk of Sudden Death [see Contraindications (4.2), Warnings and Precautions (5.3)]
- Serotonin Syndrome [see Contraindications (4.3), Warnings and Precautions (5.4), Drug Interactions (7.1)]
- Neuroleptic Malignant Syndrome (NMS) [see Warnings and Precautions (5.5)]
- Severe Cutaneous Adverse Reactions [see Warnings and Precautions (5.6)]
- Tardive Dyskinesia [see Warnings and Precautions (5.7)]
- Metabolic Changes [see Warnings and Precautions (5.8)]
- Rash [see Warnings and Precautions (5.9)]
- Orthostatic Hypotension [see Warnings and Precautions (5.10)]
- Falls [see Warnings and Precautions (5.11)]
- Leukopenia, Neutropenia, and Agranulocytosis [see Warnings and Precautions (5.12)]
- Seizures [see Warnings and Precautions (5.13)]
- Dysphagia [see Warnings and Precautions (5.14)]
- Hyperprolactinemia [see Warnings and Precautions (5.15)]
- Potential for Cognitive and Motor Impairment [see Warnings and Precautions (5.16)]
- Priapism [see Warnings and Precautions (5.17)]
- Body Temperature Regulation [see Warnings and Precautions (5.18)]
- Suicide [see Warnings and Precautions (5.19)]

6.1 Clinical Trials Experience

Because clinical trials are conducted under widely varying conditions, adverse reaction rates observed in the clinical trials of a drug cannot be directly compared to rates in the clinical trials of another drug and may not reflect the rates observed in practice.

Clinical trials in adults for oral ziprasidone included approximately 5700 patients and/or normal subjects exposed to one or more doses of ziprasidone. Of these 5700, over 4800 were patients who participated in multiple-dose effectiveness trials, and their experience corresponded to approximately 1831 patient-years. These patients include: (1) 4331 patients who participated in multiple-dose trials, predominantly in schizophrenia, representing approximately 1698 patient-years of exposure as of February 5, 2000; and (2) 472 patients who participated in bipolar mania trials representing approximately 133 patient-years of exposure. An additional 127 patients with bipolar disorder participated in a long-term maintenance treatment study representing approximately 74.7 patient-years of exposure to ziprasidone. The conditions and duration of treatment with ziprasidone included open-label and double-blind studies, inpatient and outpatient studies, and short-term and longer-term exposure.

Clinical trials for intramuscular ziprasidone included 570 patients and/or normal subjects who received one or more injections of ziprasidone. Over 325 of these subjects participated in trials involving the administration of multiple doses.

Adverse reactions during exposure were obtained by collecting voluntarily reported adverse experiences, as well as results of physical examinations, vital signs, weights, laboratory analyses, ECGs, and results of ophthalmologic examinations.

The stated frequencies of adverse reactions represent the proportion of individuals who experienced, at least once, a treatment-emergent adverse reaction of the type listed. A reaction was considered treatment-emergent if it occurred for the first time or worsened while receiving therapy following baseline evaluation.

Adverse Findings Observed in Short-Term, Placebo-Controlled Trials with Oral Ziprasidone

The following findings are based on the short-term placebo-controlled premarketing trials for schizophrenia (a pool of two 6-week, and two 4-week fixed-dose trials) and bipolar mania (a pool of two 3-week flexible-dose trials) in which ziprasidone was administered in doses ranging from 10 to 200 mg/day.

Commonly Observed Adverse Reactions in Short Term-Placebo-Controlled Trials

The following adverse reactions were the most commonly observed adverse reactions associated with the use of ziprasidone (incidence of 5% or greater) and not observed at an equivalent incidence among placebo-treated patients (ziprasidone incidence at least twice that for placebo):

Schizophrenia trials (see Table 11)

- Somnolence
- Respiratory Tract Infection

Bipolar trials (see Table 12)

- Somnolence
- Extrapyramidal Symptoms which includes the following adverse reaction terms: extrapyramidal syndrome, hypertonia, dystonia, dyskinesia, hypokinesia, tremor, paralysis and twitching. None of these adverse reactions occurred individually at an incidence greater than 10% in bipolar mania trials.
- Dizziness which includes the adverse reaction terms dizziness and lightheadedness.
- Akathisia
- Abnormal Vision
- Asthenia
- Vomiting

SCHIZOPHRENIA

Adverse Reactions Associated with Discontinuation of Treatment in Short-Term, Placebo-Controlled Trials of Oral Ziprasidone

Approximately 4.1% (29/702) of ziprasidone-treated patients in short-term, placebo-controlled studies discontinued treatment due to an adverse reaction, compared with about 2.2% (6/273) on placebo. The most common reaction associated with dropout was rash, including 7 dropouts for rash among ziprasidone patients (1%) compared to no placebo patients [see Warnings and Precautions (5.9)].

Adverse Reactions Occurring at an Incidence of 2% or More Among Ziprasidone-Treated Patients in Short-Term, Oral, Placebo-Controlled Trials

Table 11 enumerates the incidence, rounded to the nearest percent, of treatment-emergent adverse reactions that occurred during acute therapy (up to 6 weeks) in predominantly patients with schizophrenia, including only those reactions that occurred in 2% or more of patients treated with ziprasidone and for which the incidence in patients treated with ziprasidone was greater than the incidence in placebo-treated patients.

Table 11: Treatment-Emergent Adverse Reaction Incidence in Short-Term Oral Placebo-Controlled Trials – Schizophrenia
 | Percentage of Patients Reporting Reaction
Body System/Adverse Reaction | Ziprasidone; (N=702) | Placebo; (N=273)
Body as a Whole
Asthenia | 5 | 3
Accidental Injury | 4 | 2
Chest Pain | 3 | 2
Cardiovascular
Tachycardia | 2 | 1
Digestive
Nausea | 10 | 7
Constipation | 9 | 8
Dyspepsia | 8 | 7
Diarrhea | 5 | 4
Dry Mouth | 4 | 2
Anorexia | 2 | 1
Nervous
Extrapyramidal Symptoms [Extrapyramidal Symptoms includes the following adverse reaction terms: extrapyramidal syndrome, hypertonia, dystonia, dyskinesia, hypokinesia, tremor, paralysis and twitching. None of these adverse reactions occurred individually at an incidence greater than 5% in schizophrenia trials.] | 14 | 8
Somnolence | 14 | 7
Akathisia | 8 | 7
Dizziness [Dizziness includes the adverse reaction terms dizziness and lightheadedness.] | 8 | 6
Respiratory
Respiratory Tract Infection | 8 | 3
Rhinitis | 4 | 2
Cough Increased | 3 | 1
Skin and Appendages
Rash | 4 | 3
Fungal Dermatitis | 2 | 1
Special Senses
Abnormal Vision | 3 | 2

Dose Dependency of Adverse Reactions in Short-Term, Fixed-Dose, Placebo-Controlled Trials

An analysis for dose response in the schizophrenia 4-study pool revealed an apparent relation of adverse reaction to dose for the following reactions: asthenia, postural hypotension, anorexia, dry mouth, increased salivation, arthralgia, anxiety, dizziness, dystonia, hypertonia, somnolence, tremor, rhinitis, rash, and abnormal vision.

Extrapyramidal Symptoms (EPS)

The incidence of reported EPS (which included the adverse reaction terms extrapyramidal syndrome, hypertonia, dystonia, dyskinesia, hypokinesia, tremor, paralysis and twitching) for ziprasidone-treated patients in the short-term, placebo-controlled schizophrenia trials was 14% vs. 8% for placebo. Objectively collected data from those trials on the Simpson-Angus Rating Scale (for EPS) and the Barnes Akathisia Scale (for akathisia) did not generally show a difference between ziprasidone and placebo.

Dystonia

Class Effect: Symptoms of dystonia, prolonged abnormal contractions of muscle groups, may occur in susceptible individuals during the first few days of treatment. Dystonic symptoms include: spasm of the neck muscles, sometimes progressing to tightness of the throat, swallowing difficulty, difficulty breathing, and/or protrusion of the tongue. While these symptoms can occur at low doses, they occur more frequently and with greater severity with high potency and at higher doses of first generation antipsychotic drugs. An elevated risk of acute dystonia is observed in males and younger age groups.

Vital Sign Changes

Ziprasidone is associated with orthostatic hypotension [see Warnings and Precautions (5.10)].

ECG Changes

Ziprasidone is associated with an increase in the QTc interval [see Warnings and Precautions (5.3)]. In the schizophrenia trials, ziprasidone was associated with a mean increase in heart rate of 1.4 beats per minute compared to a 0.2 beats per minute decrease among placebo patients.

Other Adverse Reactions Observed During the Premarketing Evaluation of Oral Ziprasidone

Following is a list of COSTART terms that reflect treatment-emergent adverse reactions as defined in the introduction to the ADVERSE REACTIONS section reported by patients treated with ziprasidone in schizophrenia trials at multiple doses >4 mg/day within the database of 3834 patients. All reported reactions are included except those already listed in Table 11 or elsewhere in labeling, those reaction terms that were so general as to be uninformative, reactions reported only once and that did not have a substantial probability of being acutely life-threatening, reactions that are part of the illness being treated or are otherwise common as background reactions, and reactions considered unlikely to be drug-related. It is important to emphasize that, although the reactions reported occurred during treatment with ziprasidone, they were not necessarily caused by it.

Adverse reactions are further categorized by body system and listed in order of decreasing frequency according to the following definitions:

Frequent - adverse reactions occurring in at least 1/100 patients (≥1.0% of patients) (only those not already listed in the tabulated results from placebo-controlled trials appear in this listing);

Infrequent - adverse reactions occurring in 1/100 to 1/1000 patients (in 0.1-1.0% of patients)

Rare - adverse reactions occurring in fewer than 1/1000 patients (<0.1% of patients).

Body as a Whole

Frequent abdominal pain, flu syndrome, fever, accidental fall, face edema, chills, photosensitivity reaction, flank pain, hypothermia, motor vehicle accident

Cardiovascular System

Frequent tachycardia, hypertension, postural hypotension

Infrequent bradycardia, angina pectoris, atrial fibrillation

Rare first degree AV block, bundle branch block, phlebitis, pulmonary embolus, cardiomegaly, cerebral infarct, cerebrovascular accident, deep thrombophlebitis, myocarditis, thrombophlebitis

Digestive System

Frequent anorexia, vomiting

Infrequent rectal hemorrhage, dysphagia, tongue edema

Rare gum hemorrhage, jaundice, fecal impaction, gamma glutamyl transpeptidase increased, hematemesis, cholestatic jaundice, hepatitis, hepatomegaly, leukoplakia of mouth, fatty liver deposit, melena

Endocrine

Rare hypothyroidism, hyperthyroidism, thyroiditis

Hemic and Lymphatic System

Infrequent anemia, ecchymosis, leukocytosis, leukopenia, eosinophilia, lymphadenopathy

Rare thrombocytopenia, hypochromic anemia, lymphocytosis, monocytosis, basophilia, lymphedema, polycythemia, thrombocythemia

Metabolic and Nutritional Disorders

Infrequent thirst, transaminase increased, peripheral edema, hyperglycemia, creatine phosphokinase increased, alkaline phosphatase increased, hypercholesteremia, dehydration, lactic dehydrogenase increased, albuminuria, hypokalemia

Rare BUN increased, creatinine increased, hyperlipemia, hypocholesteremia, hyperkalemia, hypochloremia, hypoglycemia, hyponatremia, hypoproteinemia, glucose tolerance decreased, gout, hyperchloremia, hyperuricemia, hypocalcemia, hypoglycemic reaction, hypomagnesemia, ketosis, respiratory alkalosis

Musculoskeletal System

Frequent myalgia

Infrequent tenosynovitis

Rare myopathy

Nervous System

Frequent agitation, extrapyramidal syndrome, tremor, dystonia, hypertonia, dyskinesia, hostility, twitching, paresthesia, confusion, vertigo, hypokinesia, hyperkinesia, abnormal gait, oculogyric crisis, hypesthesia, ataxia, amnesia, cogwheel rigidity, delirium, hypotonia, akinesia, dysarthria, withdrawal syndrome, buccoglossal syndrome, choreoathetosis, diplopia, incoordination, neuropathy

Infrequent paralysis

Rare myoclonus, nystagmus, torticollis, circumoral paresthesia, opisthotonos, reflexes increased, trismus

Respiratory System

Frequent dyspnea

Infrequent pneumonia, epistaxis

Rare hemoptysis, laryngismus

Skin and Appendages

Infrequent maculopapular rash, urticaria, alopecia, eczema, exfoliative dermatitis, contact dermatitis, vesiculobullous rash

Special Senses

Frequent fungal dermatitis

Infrequent conjunctivitis, dry eyes, tinnitus, blepharitis, cataract, photophobia

Rare eye hemorrhage, visual field defect, keratitis, keratoconjunctivitis

Urogenital System

Infrequent impotence, abnormal ejaculation, amenorrhea, hematuria, menorrhagia, female lactation, polyuria, urinary retention metrorrhagia, male sexual dysfunction, anorgasmia, glycosuria

Rare gynecomastia, vaginal hemorrhage, nocturia, oliguria, female sexual dysfunction, uterine hemorrhage

BIPOLAR DISORDER

Acute Treatment of Manic or Mixed Episodes in Adults

Adverse Reactions Associated with Discontinuation of Treatment in Short Term, Placebo-Controlled Trials

Approximately 6.5% (18/279) of ziprasidone-treated patients in short-term, placebo-controlled studies discontinued treatment due to an adverse reaction, compared with about 3.7% (5/136) on placebo. The most common reactions associated with dropout in the ziprasidone-treated patients were akathisia, anxiety, depression, dizziness, dystonia, rash and vomiting, with 2 dropouts for each of these reactions among ziprasidone patients (1%) compared to one placebo patient each for dystonia and rash (1%) and no placebo patients for the remaining adverse reactions.

Adverse Reactions Occurring at an Incidence of 2% or More Among Ziprasidone-Treated Patients in Short-Term, Oral, Placebo-Controlled Trials

Table 12 enumerates the incidence, rounded to the nearest percent, of treatment-emergent adverse reactions that occurred during acute therapy (up to 3 weeks) in patients with bipolar mania, including only those reactions that occurred in 2% or more of patients treated with ziprasidone and for which the incidence in patients treated with ziprasidone was greater than the incidence in placebo-treated patients.

Table 12: Treatment-Emergent Adverse Reactions Incidence in Short-Term Oral Placebo-Controlled Trials – Manic and Mixed Episodes Associated with Bipolar Disorder
 | Percentage of Patients Reporting Reaction
Body System/Adverse Reaction | Ziprasidone; (N=279) | Placebo; (N=136)
Body as a Whole
Headache | 18 | 17
Asthenia | 6 | 2
Accidental Injury | 4 | 1
Cardiovascular
Hypertension | 3 | 2
Digestive
Nausea | 10 | 7
Diarrhea | 5 | 4
Dry Mouth | 5 | 4
Vomiting | 5 | 2
Increased Salivation | 4 | 0
Tongue Edema | 3 | 1
Dysphagia | 2 | 0
Musculoskeletal
Myalgia | 2 | 0
Nervous
Somnolence | 31 | 12
Extrapyramidal Symptoms [Extrapyramidal Symptoms includes the following adverse reaction terms: extrapyramidal syndrome, hypertonia, dystonia, dyskinesia, hypokinesia, tremor, paralysis and twitching. None of these adverse reactions occurred individually at an incidence greater than 10% in bipolar mania trials.] | 31 | 12
Dizziness [Dizziness includes the adverse reaction terms dizziness and lightheadedness.] | 16 | 7
Akathisia | 10 | 5
Anxiety | 5 | 4
Hypesthesia | 2 | 1
Speech Disorder | 2 | 0
Respiratory
Pharyngitis | 3 | 1
Dyspnea | 2 | 1
Skin and Appendages
Fungal Dermatitis | 2 | 1
Special Senses
Abnormal Vision | 6 | 3

Explorations for interactions on the basis of gender did not reveal any clinically meaningful differences in the adverse reaction occurrence on the basis of this demographic factor.

INTRAMUSCULAR ZIPRASIDONE

Adverse Reactions Occurring at an Incidence of 1% or More Among Ziprasidone-Treated Patients in Short-Term Trials of Intramuscular Ziprasidone

Table 13 enumerates the incidence, rounded to the nearest percent, of treatment-emergent adverse reactions that occurred during acute therapy with intramuscular ziprasidone in 1% or more of patients.

In these studies, the most commonly observed adverse reactions associated with the use of intramuscular ziprasidone (incidence of 5% or greater) and observed at a rate on intramuscular ziprasidone (in the higher dose groups) at least twice that of the lowest intramuscular ziprasidone group were headache (13%), nausea (12%), and somnolence (20%).

Table 13: Treatment-Emergent Adverse Reaction Incidence in Short-Term Fixed-Dose Intramuscular Trials
 | Percentage of Patients Reporting Reaction
Body System/Adverse Reaction | Ziprasidone 2 mg (N=92) | Ziprasidone 10 mg (N=63) | Ziprasidone 20 mg (N=41)
Body as a Whole
Headache | 3 | 13 | 5
Injection Site Pain | 9 | 8 | 7
Asthenia | 2 | 0 | 0
Abdominal Pain | 0 | 2 | 0
Flu Syndrome | 1 | 0 | 0
Back Pain | 1 | 0 | 0
Cardiovascular
Postural Hypotension | 0 | 0 | 5
Hypertension | 2 | 0 | 0
Bradycardia | 0 | 0 | 2
Vasodilation | 1 | 0 | 0
Digestive
Nausea | 4 | 8 | 12
Rectal Hemorrhage | 0 | 0 | 2
Diarrhea | 3 | 3 | 0
Vomiting | 0 | 3 | 0
Dyspepsia | 1 | 3 | 2
Anorexia | 0 | 2 | 0
Constipation | 0 | 0 | 2
Tooth Disorder | 1 | 0 | 0
Dry Mouth | 1 | 0 | 0
Nervous
Dizziness | 3 | 3 | 10
Anxiety | 2 | 0 | 0
Insomnia | 3 | 0 | 0
Somnolence | 8 | 8 | 20
Akathisia | 0 | 2 | 0
Agitation | 2 | 2 | 0
Extrapyramidal Syndrome | 2 | 0 | 0
Hypertonia | 1 | 0 | 0
Cogwheel Rigidity | 1 | 0 | 0
Paresthesia | 0 | 2 | 0
Personality Disorder | 0 | 2 | 0
Psychosis | 1 | 0 | 0
Speech Disorder | 0 | 2 | 0
Respiratory
Rhinitis | 1 | 0 | 0
Skin and Appendages
Furunculosis | 0 | 2 | 0
Sweating | 0 | 0 | 2
Urogenital
Dysmenorrhea | 0 | 2 | 0
Priapism | 1 | 0 | 0

6.2 Postmarketing Experience

The following adverse reactions have been identified during post-approval use of GEODON. Because these reactions are reported voluntarily from a population of uncertain size, it is not always possible to reliably estimate their frequency or establish a causal relationship to drug exposure.

Adverse reaction reports not listed above that have been received since market introduction include rare occurrences of the following : Cardiac Disorders: Tachycardia, torsade de pointes (in the presence of multiple confounding factors), [see Warnings and Precautions (5.3)]; Digestive System Disorders: Swollen Tongue; Reproductive System and Breast Disorders: Galactorrhea, priapism; Nervous System Disorders: Facial Droop, neuroleptic malignant syndrome, serotonin syndrome (alone or in combination with serotonergic medicinal products), tardive dyskinesia; Psychiatric Disorders: Insomnia, mania/hypomania, somnambulism; Skin and subcutaneous Tissue Disorders: Allergic reaction (such as allergic dermatitis, angioedema, orofacial edema, urticaria), rash, Drug Reaction with Eosinophilia and Systemic Symptoms (DRESS); Urogenital System Disorders: Enuresis, urinary incontinence; Vascular Disorders: Postural hypotension, syncope.

7 DRUG INTERACTIONS

Drug-drug interactions can be pharmacodynamic (combined pharmacologic effects) or pharmacokinetic (alteration of plasma levels). The risks of using ziprasidone in combination with other drugs have been evaluated as described below. All interactions studies have been conducted with oral ziprasidone. Based upon the pharmacodynamic and pharmacokinetic profile of ziprasidone, possible interactions could be anticipated:

7.1 Metabolic Pathway

Approximately two-thirds of ziprasidone is metabolized via a combination of chemical reduction by glutathione and enzymatic reduction by aldehyde oxidase. There are no known clinically relevant inhibitors or inducers of aldehyde oxidase. Less than one-third of ziprasidone metabolic clearance is mediated by cytochrome P450 catalyzed oxidation.

7.2 In Vitro Studies

An in vitro enzyme inhibition study utilizing human liver microsomes showed that ziprasidone had little inhibitory effect on CYP1A2, CYP2C9, CYP2C19, CYP2D6 and CYP3A4, and thus would not likely interfere with the metabolism of drugs primarily metabolized by these enzymes. There is little potential for drug interactions with ziprasidone due to displacement [see Clinical Pharmacology (12.3)].

7.3 Pharmacodynamic Interactions

- Ziprasidone should not be used with any drug that prolongs the QT interval [see Contraindications (4.1)].
- Given the primary CNS effects of ziprasidone, caution should be used when it is taken in combination with other centrally acting drugs.
- Because of its potential for inducing hypotension, ziprasidone may enhance the effects of certain antihypertensive agents.
- Ziprasidone may antagonize the effects of levodopa and dopamine agonists.
- Risk of serotonin syndrome with concomitant therapy with other serotonergic drugs such as SNRIs, SSRIs, triptans, tricyclic antidepressants, opioids, lithium, tryptophan, buspirone, amphetamines, and St. John’s Wort [see Contraindications (4.3), Warnings and Precautions (5.4), Adverse Reactions (6.2)].

7.4 Pharmacokinetic Interactions

Carbamazepine

Carbamazepine is an inducer of CYP3A4; administration of 200 mg twice daily for 21 days resulted in a decrease of approximately 35% in the AUC of ziprasidone. This effect may be greater when higher doses of carbamazepine are administered.

Ketoconazole

Ketoconazole, a potent inhibitor of CYP3A4, at a dose of 400 mg QD for 5 days, increased the AUC and Cmax of ziprasidone by about 35-40%. Other inhibitors of CYP3A4 would be expected to have similar effects.

Cimetidine

Cimetidine at a dose of 800 mg QD for 2 days did not affect ziprasidone pharmacokinetics.

Antacid

The co-administration of 30 mL of Maalox® with ziprasidone did not affect the pharmacokinetics of ziprasidone.

7.5 Lithium

Ziprasidone at a dose of 40 mg twice daily administered concomitantly with lithium at a dose of 450 mg twice daily for 7 days did not affect the steady-state level or renal clearance of lithium. Ziprasidone dosed adjunctively to lithium in a maintenance trial of bipolar patients did not affect mean therapeutic lithium levels.

7.6 Oral Contraceptives

In vivo studies have revealed no effect of ziprasidone on the pharmacokinetics of estrogen or progesterone components. Ziprasidone at a dose of 20 mg twice daily did not affect the pharmacokinetics of concomitantly administered oral contraceptives, ethinyl estradiol (0.03 mg) and levonorgestrel (0.15 mg).

7.7 Dextromethorphan

Consistent with in vitro results, a study in normal healthy volunteers showed that ziprasidone did not alter the metabolism of dextromethorphan, a CYP2D6 model substrate, to its major metabolite, dextrorphan. There was no statistically significant change in the urinary dextromethorphan/dextrorphan ratio.

7.8 Valproate

A pharmacokinetic interaction of ziprasidone with valproate is unlikely due to the lack of common metabolic pathways for the two drugs. Ziprasidone dosed adjunctively to valproate in a maintenance trial of bipolar patients did not affect mean therapeutic valproate levels.

7.9 Other Concomitant Drug Therapy

Population pharmacokinetic analysis of schizophrenic patients enrolled in controlled clinical trials has not revealed evidence of any clinically significant pharmacokinetic interactions with benztropine, propranolol, or lorazepam.

7.10 Food Interaction

The absolute bioavailability of a 20 mg dose under fed conditions is approximately 60%. The absorption of ziprasidone is increased up to two-fold in the presence of food [see Clinical Pharmacology (12.3)].

8 USE IN SPECIFIC POPULATIONS

8.1 Pregnancy

Pregnancy Exposure Registry

There is a pregnancy exposure registry that monitors pregnancy outcomes in women exposed to atypical antipsychotics, including GEODON, during pregnancy. Healthcare providers are encouraged to register patients by contacting the National Pregnancy Registry for Atypical Antipsychotics at 1-866-961-2388 or online at http://womensmentalhealth.org/clinical-and-research-programs/pregnancyregistry/.

Risk Summary

Neonates exposed to antipsychotic drugs, including GEODON, during the third trimester are at risk for extrapyramidal and/or withdrawal symptoms following delivery (see Clinical Considerations). Overall available data from published epidemiologic studies of pregnant women exposed to ziprasidone have not established a drug-associated risk of major birth defects, miscarriage, or adverse maternal or fetal outcomes (see Data). There are risks to the mother associated with untreated schizophrenia or bipolar I disorder and with exposure to antipsychotics, including GEODON, during pregnancy (see Clinical Considerations).

In animal studies, ziprasidone administration to pregnant rats and rabbits during organogenesis caused developmental toxicity at doses similar to recommended human doses, and was teratogenic in rabbits at 3 times the maximum recommended human dose (MRHD). Rats exposed to ziprasidone during gestation and lactation exhibited increased perinatal pup mortality and delayed neurobehavioral and functional development of offspring at doses less than or similar to human therapeutic doses. (see Data).

The estimated background risk of major birth defects and miscarriage for the indicated populations is unknown. All pregnancies have a background risk of birth defect, loss, or other adverse outcomes. In the U.S. general population, the estimated background risk of major birth defects and miscarriage in clinically recognized pregnancies is 2 to 4% and 15 to 20%, respectively.

Clinical Considerations

Disease-associated Maternal and/or Embryo/Fetal Risk

There is risk to the mother from untreated schizophrenia or bipolar I disorder, including increased risk of relapse, hospitalization, and suicide. Schizophrenia and bipolar I disorder are associated with increased adverse perinatal outcomes, including preterm birth. It is not known if this is a direct result of the illness or other comorbid factors.

Fetal/Neonatal Adverse Reactions

Extrapyramidal and/or withdrawal symptoms, including agitation, hypertonia, hypotonia, tremor, somnolence, respiratory distress, and feeding disorder have been reported in neonates who were exposed to antipsychotic drugs, including GEODON, during the third trimester of pregnancy. These symptoms have varied in severity. Monitor neonates for extrapyramidal and/or withdrawal symptoms and manage symptoms appropriately. Some neonates recovered within hours or days without specific treatment; others required prolonged hospitalization.

Data

Human Data

Published data from observational studies, birth registries, and case reports on the use of atypical antipsychotics during pregnancy do not report a clear association with antipsychotics and major birth defects. A retrospective cohort study from a Medicaid database of 9258 women exposed to antipsychotics during pregnancy did not indicate an overall increased risk for major birth defects.

Animal Data

When ziprasidone was administered to pregnant rabbits during the period of organogenesis, an increased incidence of fetal structural abnormalities (ventricular septal defects and other cardiovascular malformations, and kidney alterations) was observed at a dose of 30 mg/kg/day (3 times the MRHD of 200 mg/day based on mg/m^2 body surface area). There was no evidence to suggest that these developmental effects were secondary to maternal toxicity. The developmental no effect dose was 10 mg/kg/day (equivalent to the MRHD based on a mg/m^2 body surface area). In rats, embryofetal toxicity (decreased fetal weights, delayed skeletal ossification) was observed following administration of 10 to 160 mg/kg/day (0.5 to 8 times the MRHD based on mg/m^2 body surface area) during organogenesis or throughout gestation, but there was no evidence of teratogenicity. Doses of 40 and 160 mg/kg/day (2 and 8 times the MRHD based on mg/m^2 body surface area) were associated with maternal toxicity. The developmental no-effect dose is 5 mg/kg/day (0.2 times the MRHD based on mg/m^2 body surface area).

There was an increase in the number of pups born dead and a decrease in postnatal survival through the first 4 days of lactation among the offspring of female rats treated during gestation and lactation with doses of 10 mg/kg/day (0.5 times the MRHD based on mg/m^2 body surface area) or greater. Offspring developmental delays (decreased pup weights) and neurobehavioral functional impairment (eye opening air righting) were observed at doses of 5 mg/kg/day (0.2 times the MRHD based on mg/m^2 body surface area) or greater. A no-effect level was not established for these effects.

8.2 Lactation

Risk Summary

Limited data from a published case report indicate the presence of ziprasidone in human milk. Although there are no reports of adverse effects on a breastfed infant exposed to ziprasidone via breast milk, there are reports of excess sedation, irritability, poor feeding, and extrapyramidal symptoms (tremors and abnormal muscle movements) in infants exposed to other atypical antipsychotics through breast milk (see Clinical Considerations). There is no information on the effects of ziprasidone on milk production. The developmental and health benefits of breastfeeding should be considered along with the mother’s clinical need for GEODON and any potential adverse effects on the breastfed child from GEODON or from the mother’s underlying condition.

Clinical Considerations

Infants exposed to GEODON should be monitored for excess sedation, irritability, poor feeding, and extrapyramidal symptoms (tremors and abnormal muscle movements).

8.3 Females and Males of Reproductive Potential

Infertility

Females

Based on the pharmacologic action of ziprasidone (D2 antagonism), treatment with GEODON may result in an increase in serum prolactin levels, which may lead to a reversible reduction in fertility in females of reproductive potential [see Warnings and Precautions (5.15) and Nonclinical Toxicology (13.1)].

8.4 Pediatric Use

The safety and effectiveness of Geodon have not been established in pediatric patients.

Geodon was studied in one 4-week, placebo-controlled trial in patients 10 to 17 years of age with bipolar I disorder. However, the data were insufficient to fully assess the safety of Geodon in pediatric patients. Therefore, a safe and effective dose for use could not be established.

8.5 Geriatric Use

Of the total number of subjects in clinical studies of ziprasidone, 2.4 percent were 65 and over. No overall differences in safety or effectiveness were observed between these subjects and younger subjects, and other reported clinical experience has not identified differences in responses between the elderly and younger patients, but greater sensitivity of some older individuals cannot be ruled out. Nevertheless, the presence of multiple factors that might increase the pharmacodynamic response to ziprasidone, or cause poorer tolerance or orthostasis, should lead to consideration of a lower starting dose, slower titration, and careful monitoring during the initial dosing period for some elderly patients.

Ziprasidone intramuscular has not been systematically evaluated in elderly patients (65 years and over).

8.6 Renal Impairment

Because ziprasidone is highly metabolized, with less than 1% of the drug excreted unchanged, renal impairment alone is unlikely to have a major impact on the pharmacokinetics of ziprasidone. The pharmacokinetics of ziprasidone following 8 days of 20 mg twice daily dosing were similar among subjects with varying degrees of renal impairment (n=27), and subjects with normal renal function, indicating that dosage adjustment based upon the degree of renal impairment is not required. Ziprasidone is not removed by hemodialysis.

Intramuscular ziprasidone has not been systematically evaluated in elderly patients or in patients with hepatic or renal impairment. As the cyclodextrin excipient is cleared by renal filtration, ziprasidone intramuscular should be administered with caution to patients with impaired renal function [see Clinical Pharmacology (12)].

8.7 Hepatic Impairment

As ziprasidone is cleared substantially by the liver, the presence of hepatic impairment would be expected to increase the AUC of ziprasidone; a multiple-dose study at 20 mg twice daily for 5 days in subjects (n=13) with clinically significant (Childs-Pugh Class A and B) cirrhosis revealed an increase in AUC 0-12 of 13% and 34% in Childs-Pugh Class A and B, respectively, compared to a matched control group (n=14). A half-life of 7.1 hours was observed in subjects with cirrhosis compared to 4.8 hours in the control group.

8.8 Age and Gender Effects

In a multiple-dose (8 days of treatment) study involving 32 subjects, there was no difference in the pharmacokinetics of ziprasidone between men and women or between elderly (>65 years) and young (18 to 45 years) subjects. Additionally, population pharmacokinetic evaluation of patients in controlled trials has revealed no evidence of clinically significant age or gender-related differences in the pharmacokinetics of ziprasidone. Dosage modifications for age or gender are, therefore, not recommended.

8.9 Smoking

Based on in vitro studies utilizing human liver enzymes, ziprasidone is not a substrate for CYP1A2; smoking should therefore not have an effect on the pharmacokinetics of ziprasidone. Consistent with these in vitro results, population pharmacokinetic evaluation has not revealed any significant pharmacokinetic differences between smokers and nonsmokers.

9 DRUG ABUSE AND DEPENDENCE

9.3 Dependence

Ziprasidone has not been systematically studied, in animals or humans, for its potential for abuse, tolerance, or physical dependence. While the clinical trials did not reveal any tendency for drug-seeking behavior, these observations were not systematic and it is not possible to predict on the basis of this limited experience the extent to which ziprasidone will be misused, diverted, and/or abused once marketed. Consequently, patients should be evaluated carefully for a history of drug abuse, and such patients should be observed closely for signs of ziprasidone misuse or abuse (e.g., development of tolerance, increases in dose, drug-seeking behavior).

10 OVERDOSAGE

10.1 Human Experience

In premarketing trials involving more than 5400 patients and/or normal subjects, accidental or intentional overdosage of oral ziprasidone was documented in 10 patients. All of these patients survived without sequelae. In the patient taking the largest confirmed amount, 3,240 mg, the only symptoms reported were minimal sedation, slurring of speech, and transitory hypertension (200/95).

Adverse reactions reported with ziprasidone overdose included extrapyramidal symptoms, somnolence, tremor, and anxiety. [see Adverse Reactions (6.2)]

10.2 Management of Overdosage

In case of acute overdosage, establish and maintain an airway and ensure adequate oxygenation and ventilation. Intravenous access should be established, and gastric lavage (after intubation, if patient is unconscious) and administration of activated charcoal together with a laxative should be considered. The possibility of obtundation, seizure, or dystonic reaction of the head and neck following overdose may create a risk of aspiration with induced emesis.

Cardiovascular monitoring should commence immediately and should include continuous electrocardiographic monitoring to detect possible arrhythmias. If antiarrhythmic therapy is administered, disopyramide, procainamide, and quinidine carry a theoretical hazard of additive QT-prolonging effects that might be additive to those of ziprasidone.

Hypotension and circulatory collapse should be treated with appropriate measures such as intravenous fluids. If sympathomimetic agents are used for vascular support, epinephrine and dopamine should not be used, since beta stimulation combined with α1 antagonism associated with ziprasidone may worsen hypotension. Similarly, it is reasonable to expect that the alpha-adrenergic-blocking properties of bretylium might be additive to those of ziprasidone, resulting in problematic hypotension.

In cases of severe extrapyramidal symptoms, anticholinergic medication should be administered. There is no specific antidote to ziprasidone, and it is not dialyzable. The possibility of multiple drug involvement should be considered. Close medical supervision and monitoring should continue until the patient recovers.

11 DESCRIPTION

GEODON contains the active moiety, ziprasidone, in either the form of ziprasidone hydrochloride salt for capsules and in the form of ziprasidone mesylate salt for intramuscular use only. Ziprasidone is a psychotropic agent that is chemically unrelated to phenothiazine or butyrophenone antipsychotic agents. It has a molecular weight of 412.94 (free base), with the following chemical name: 5-[2-[4-(1,2-benzisothiazol-3-yl)-1-piperazinyl]ethyl]-6-chloro-1,3-dihydro-2H-indol-2-one. The empirical formula of C21H21ClN4OS (free base of ziprasidone) represents the following structural formula:

GEODON capsules contain a monohydrochloride, monohydrate salt of ziprasidone. Chemically, ziprasidone hydrochloride monohydrate is 5-[2-[4-(1,2-benzisothiazol-3-yl)-1-piperazinyl]ethyl]-6-chloro-1,3-dihydro-2H-indol-2-one, monohydrochloride, monohydrate. The empirical formula is C21H21ClN4OS · HCl · H2O and its molecular weight is 467.42. Ziprasidone hydrochloride monohydrate is a white to slightly pink powder.

GEODON capsules are supplied for oral administration in 20 mg (blue/white), 40 mg (blue/blue), 60 mg (white/white), and 80 mg (blue/white) capsules. GEODON capsules contain ziprasidone hydrochloride monohydrate, lactose, magnesium stearate and pregelatinized starch. Each capsule for oral use contains ziprasidone hydrochloride monohydrate equivalent to either 20 mg, 40 mg, 60 mg, or 80 mg of ziprasidone.

GEODON for Injection contains a lyophilized form of ziprasidone mesylate trihydrate. Chemically, ziprasidone mesylate trihydrate is 5-[2-[4-(1,2-benzisothiazol-3-yl)-1-piperazinyl]ethyl]-6-chloro-1,3-dihydro-2H-indol-2-one, methanesulfonate, trihydrate. The empirical formula is C21H21ClN4OS · CH3SO3H · 3H2O and its molecular weight is 563.09.

GEODON for Injection is available in a single-dose vial as ziprasidone mesylate (20 mg ziprasidone/mL when reconstituted according to label instructions) [see Dosage and Administration (2.4)]. Each mL of ziprasidone mesylate for injection (when reconstituted) contains 20 mg of ziprasidone and 4.7 mg of methanesulfonic acid solubilized by 294 mg of sulfobutylether β-cyclodextrin sodium (SBECD).

12 CLINICAL PHARMACOLOGY

12.1 Mechanism of Action

The mechanism of action of ziprasidone in the treatment of the listed indications could be mediated through a combination of dopamine type 2 (D2) and serotonin type 2 (5HT2) antagonism.

12.2 Pharmacodynamics

Ziprasidone binds with relatively high affinity to the dopamine D2 and D3, serotonin 5HT2A, 5HT2C, 5HT1A, 5HT1D, and α1-adrenergic receptors (Kis of 4.8, 7.2, 0.4, 1.3, 3.4, 2, and 10 nM, respectively), and with moderate affinity to the histamine H1 receptor (Ki=47 nM). Ziprasidone is an antagonist at the D2, 5HT2A, and 5HT1D receptors, and an agonist at the 5HT1A receptor. Ziprasidone inhibited synaptic reuptake of serotonin and norepinephrine. No appreciable affinity was exhibited for other receptor/binding sites tested, including the cholinergic muscarinic receptor (IC50 >1 μM).

12.3 Pharmacokinetics

Oral Pharmacokinetics

Ziprasidone’s activity is primarily due to the parent drug. The multiple-dose pharmacokinetics of ziprasidone are dose-proportional within the proposed clinical dose range, and ziprasidone accumulation is predictable with multiple dosing. Elimination of ziprasidone is mainly via hepatic metabolism with a mean terminal half-life of about 7 hours within the proposed clinical dose range. Steady-state concentrations are achieved within one to three days of dosing. The mean apparent systemic clearance is 7.5 mL/min/kg. Ziprasidone is unlikely to interfere with the metabolism of drugs metabolized by cytochrome P450 enzymes.

Absorption: Ziprasidone is well absorbed after oral administration, reaching peak plasma concentrations in 6 to 8 hours. The absolute bioavailability of a 20 mg dose under fed conditions is approximately 60%. The absorption of ziprasidone is increased up to two-fold in the presence of food.

Distribution: Ziprasidone has a mean apparent volume of distribution of 1.5 L/kg. It is greater than 99% bound to plasma proteins, binding primarily to albumin and α1-acid glycoprotein. The in vitro plasma protein binding of ziprasidone was not altered by warfarin or propranolol, two highly protein-bound drugs, nor did ziprasidone alter the binding of these drugs in human plasma. Thus, the potential for drug interactions with ziprasidone due to displacement is minimal.

Metabolism and Elimination: Ziprasidone is extensively metabolized after oral administration with only a small amount excreted in the urine (<1%) or feces (<4%) as unchanged drug. Ziprasidone is primarily cleared via three metabolic routes to yield four major circulating metabolites, benzisothiazole (BITP) sulphoxide, BITP-sulphone, ziprasidone sulphoxide, and S-methyldihydroziprasidone. Approximately 20% of the dose is excreted in the urine, with approximately 66% being eliminated in the feces. Unchanged ziprasidone represents about 44% of total drug-related material in serum. In vitro studies using human liver subcellular fractions indicate that S-methyldihydroziprasidone is generated in two steps. These studies indicate that the reduction reaction is mediated primarily by chemical reduction by glutathione as well as by enzymatic reduction by aldehyde oxidase and the subsequent methylation is mediated by thiol methyltransferase. In vitro studies using human liver microsomes and recombinant enzymes indicate that CYP3A4 is the major CYP contributing to the oxidative metabolism of ziprasidone. CYP1A2 may contribute to a much lesser extent. Based on in vivo abundance of excretory metabolites, less than one-third of ziprasidone metabolic clearance is mediated by cytochrome P450 catalyzed oxidation and approximately two-thirds via reduction. There are no known clinically relevant inhibitors or inducers of aldehyde oxidase.

Intramuscular Pharmacokinetics

Systemic Bioavailability: The bioavailability of ziprasidone administered intramuscularly is 100%. After intramuscular administration of single doses, peak serum concentrations typically occur at approximately 60 minutes post-dose or earlier and the mean half-life (T½) ranges from two to five hours. Exposure increases in a dose-related manner and following three days of intramuscular dosing, little accumulation is observed.

Metabolism and Elimination: Although the metabolism and elimination of IM ziprasidone have not been systematically evaluated, the intramuscular route of administration would not be expected to alter the metabolic pathways.

13 NONCLINICAL TOXICOLOGY

13.1 Carcinogenesis, Mutagenesis, Impairment of Fertility

Carcinogenesis

Lifetime carcinogenicity studies were conducted with ziprasidone in Long Evans rats and CD-1 mice. Ziprasidone was administered for 24 months in the diet at doses of 2, 6, or 12 mg/kg/day to rats, and 50, 100, or 200 mg/kg/day to mice (0.1 to 0.6 and 1 to 5 times the maximum recommended human dose (MRHD) of 200 mg/day based on mg/m^2 body surface area, respectively). In the rat study, there was no evidence of an increased incidence of tumors compared to controls. In male mice, there was no increase in incidence of tumors relative to controls. In female mice, there were dose-related increases in the incidences of pituitary gland adenoma and carcinoma, and mammary gland adenocarcinoma at all doses tested (50 to 200 mg/kg/day or 1 to 5 times the MRHD based on mg/m^2 body surface area). Proliferative changes in the pituitary and mammary glands of rodents have been observed following chronic administration of other antipsychotic agents and are considered to be prolactin-mediated. Increases in serum prolactin were observed in a 1-month dietary study in female, but not male, mice at 100 and 200 mg/kg/day (or 2.5 and 5 times the MRHD based on mg/m^2 body surface area). Ziprasidone had no effect on serum prolactin in rats in a 5-week dietary study at the doses that were used in the carcinogenicity study. The relevance for human risk of the findings of prolactin-mediated endocrine tumors in rodents is unknown [see Warnings and Precautions (5.15)].

Mutagenesis

Ziprasidone was tested in the Ames bacterial mutation assay, the in vitro mammalian cell gene mutation mouse lymphoma assay, the in vitro chromosomal aberration assay in human lymphocytes, and the in vivo chromosomal aberration assay in mouse bone marrow. There was a reproducible mutagenic response in the Ames assay in one strain of S. typhimurium in the absence of metabolic activation. Positive results were obtained in both the in vitro mammalian cell gene mutation assay and the in vitro chromosomal aberration assay in human lymphocytes.

Impairment of Fertility

Ziprasidone was shown to increase time to copulation in Sprague-Dawley rats in two fertility and early embryonic development studies at doses of 10 to 160 mg/kg/day (0.5 to 8 times the MRHD of 200 mg/day based on mg/m^2 body surface area). Fertility rate was reduced at 160 mg/kg/day (8 times the MRHD based on mg/m^2 body surface area). There was no effect on fertility at 40 mg/kg/day (2 times the MRHD based on mg/m^2 body surface area). The effect on fertility appeared to be in the female since fertility was not impaired when males given 160 mg/kg/day (8 times the MRHD based on mg/m^2 body surface area) were mated with untreated females.

14 CLINICAL STUDIES

14.1 Schizophrenia

The efficacy of oral ziprasidone in the treatment of schizophrenia was evaluated in 5 placebo-controlled studies, 4 short-term (4- and 6-week) trials and one maintenance trial. All trials were in adult inpatients, most of whom met DSM III-R criteria for schizophrenia. Each study included 2 to 3 fixed doses of ziprasidone as well as placebo. Four of the 5 trials were able to distinguish ziprasidone from placebo; one short-term study did not. Although a single fixed-dose haloperidol arm was included as a comparative treatment in one of the three short-term trials, this single study was inadequate to provide a reliable and valid comparison of ziprasidone and haloperidol.

Several instruments were used for assessing psychiatric signs and symptoms in these studies. The Brief Psychiatric Rating Scale (BPRS) and the Positive and Negative Syndrome Scale (PANSS) are both multi-item inventories of general psychopathology usually used to evaluate the effects of drug treatment in schizophrenia. The BPRS psychosis cluster (conceptual disorganization, hallucinatory behavior, suspiciousness, and unusual thought content) is considered a particularly useful subset for assessing actively psychotic schizophrenic patients. A second widely used assessment, the Clinical Global Impression (CGI), reflects the impression of a skilled observer, fully familiar with the manifestations of schizophrenia, about the overall clinical state of the patient. In addition, the Scale for Assessing Negative Symptoms (SANS) was employed for assessing negative symptoms in one trial.

The results of the oral ziprasidone trials in schizophrenia follow:

- In a 4-week, placebo-controlled trial (n=139) comparing 2 fixed doses of ziprasidone (20 and 60 mg twice daily) with placebo, only the 60 mg dose was superior to placebo on the BPRS total score and the CGI severity score. This higher dose group was not superior to placebo on the BPRS psychosis cluster or on the SANS.
- In a 6-week, placebo-controlled trial (n=302) comparing 2 fixed doses of ziprasidone (40 and 80 mg twice daily) with placebo, both dose groups were superior to placebo on the BPRS total score, the BPRS psychosis cluster, the CGI severity score and the PANSS total and negative subscale scores. Although 80 mg twice daily had a numerically greater effect than 40 mg twice daily, the difference was not statistically significant.
- In a 6-week, placebo-controlled trial (n=419) comparing 3 fixed doses of ziprasidone (20, 60, and 100 mg twice daily) with placebo, all three dose groups were superior to placebo on the PANSS total score, the BPRS total score, the BPRS psychosis cluster, and the CGI severity score. Only the 100 mg twice daily dose group was superior to placebo on the PANSS negative subscale score. There was no clear evidence for a dose-response relationship within the 20 mg twice daily to 100 mg twice daily dose range.
- In a 4-week, placebo-controlled trial (n=200) comparing 3 fixed doses of ziprasidone (5, 20, and 40 mg twice daily), none of the dose groups was statistically superior to placebo on any outcome of interest.
- A study was conducted in stable chronic or subchronic (CGI-S ≤5 at baseline) schizophrenic inpatients (n=294) who had been hospitalized for not less than two months. After a 3-day single-blind placebo run-in, subjects were randomized to one of 3 fixed doses of ziprasidone (20 mg, 40 mg, or 80 mg twice daily) or placebo and observed for relapse. Patients were observed for “impending psychotic relapse,” defined as CGI-improvement score of ≥6 (much worse or very much worse) and/or scores ≥6 (moderately severe) on the hostility or uncooperativeness items of the PANSS on two consecutive days. Ziprasidone was significantly superior to placebo in time to relapse, with no significant difference between the different dose groups. There were insufficient data to examine population subsets based on age and race. Examination of population subsets based on gender did not reveal any differential responsiveness.

14.2 Bipolar I Disorder (Acute Mixed or Manic Episodes and Maintenance Treatment as an Adjunct to Lithium or Valproate)

Acute Manic and Mixed Episodes Associated with Bipolar I Disorder

The efficacy of ziprasidone was established in 2 placebo-controlled, double-blind, 3-week monotherapy studies in patients meeting DSM-IV criteria for bipolar I disorder, manic or mixed episode with or without psychotic features. Primary rating instruments used for assessing manic symptoms in these trials were: (1) the Mania Rating Scale (MRS), which is derived from the Schedule for Affective Disorders and Schizophrenia-Change Version (SADS-CB) with items grouped as the Manic Syndrome subscale (elevated mood, less need for sleep, excessive energy, excessive activity, grandiosity), the Behavior and Ideation subscale (irritability, motor hyperactivity, accelerated speech, racing thoughts, poor judgment) and impaired insight; and (2) the Clinical Global Impression-Severity of Illness Scale (CGI-S), which was used to assess the clinical significance of treatment response.

The results of the oral ziprasidone trials in adult bipolar I disorder, manic/mixed episode follow: in a 3-week placebo-controlled trial (n=210), the dose of ziprasidone was 40 mg twice daily on Day 1 and 80 mg twice daily on Day 2. Titration within the range of 40-80 mg twice daily (in 20 mg twice daily increments) was permitted for the duration of the study. Ziprasidone was significantly more effective than placebo in reduction of the MRS total score and the CGI-S score. The mean daily dose of ziprasidone in this study was 132 mg. In a second 3-week placebo-controlled trial (n=205), the dose of ziprasidone was 40 mg twice daily on Day 1. Titration within the range of 40-80 mg twice daily (in 20 mg twice daily increments) was permitted for the duration of study (beginning on Day 2). Ziprasidone was significantly more effective than placebo in reduction of the MRS total score and the CGI-S score. The mean daily dose of ziprasidone in this study was 112 mg.

Maintenance Therapy

The efficacy of ziprasidone as adjunctive therapy to lithium or valproate in the maintenance treatment of bipolar I disorder was established in a placebo-controlled trial in patients who met DSM-IV criteria for bipolar I disorder. The trial included patients whose most recent episode was manic or mixed, with or without psychotic features. In the open-label phase, patients were required to be stabilized on ziprasidone plus lithium or valproic acid for at least 8 weeks in order to be randomized. In the double-blind randomized phase, patients continued treatment with lithium or valproic acid and were randomized to receive either ziprasidone (administered twice daily totaling 80 mg to 160 mg per day) or placebo. Generally, in the maintenance phase, patients continued on the same dose on which they were stabilized during the stabilization phase. The primary endpoint in this study was time to recurrence of a mood episode (manic, mixed or depressed episode) requiring intervention, which was defined as any of the following: discontinuation due to a mood episode, clinical intervention for a mood episode (e.g., initiation of medication or hospitalization), or Mania Rating Scale score ≥18 or a MADRS score ≥18 (on 2 consecutive assessments no more than 10 days apart). A total of 584 subjects were treated in the open-label stabilization period. In the double-blind randomization period, 127 subjects were treated with ziprasidone, and 112 subjects were treated with placebo. Ziprasidone was superior to placebo in increasing the time to recurrence of a mood episode. The types of relapse events observed included depressive, manic, and mixed episodes. Depressive, manic, and mixed episodes accounted for 53%, 34%, and 13%, respectively, of the total number of relapse events in the study.

14.3 Acute Treatment of Agitation in Schizophrenia

The efficacy of intramuscular ziprasidone in the management of agitated schizophrenic patients was established in two short-term, double-blind trials of schizophrenic subjects who were considered by the investigators to be “acutely agitated” and in need of IM antipsychotic medication. In addition, patients were required to have a score of 3 or more on at least 3 of the following items of the PANSS: anxiety, tension, hostility and excitement. Efficacy was evaluated by analysis of the area under the curve (AUC) of the Behavioural Activity Rating Scale (BARS) and Clinical Global Impression (CGI) severity rating. The BARS is a seven point scale with scores ranging from 1 (difficult or unable to rouse) to 7 (violent, requires restraint). Patients' scores on the BARS at baseline were mostly 5 (signs of overt activity [physical or verbal], calms down with instructions) and as determined by investigators, exhibited a degree of agitation that warranted intramuscular therapy. There were few patients with a rating higher than 5 on the BARS, as the most severely agitated patients were generally unable to provide informed consent for participation in premarketing clinical trials.

Both studies compared higher doses of ziprasidone intramuscular with a 2 mg control dose. In one study, the higher dose was 20 mg, which could be given up to 4 times in the 24 hours of the study, at interdose intervals of no less than 4 hours. In the other study, the higher dose was 10 mg, which could be given up to 4 times in the 24 hours of the study, at interdose intervals of no less than 2 hours.

The results of the intramuscular ziprasidone trials follow:

(1) In a one-day, double-blind, randomized trial (n=79) involving doses of ziprasidone intramuscular of 20 mg or 2 mg, up to QID, ziprasidone intramuscular 20 mg was statistically superior to ziprasidone intramuscular 2 mg, as assessed by AUC of the BARS at 0 to 4 hours, and by CGI severity at 4 hours and study endpoint.
(2) In another one-day, double-blind, randomized trial (n=117) involving doses of ziprasidone intramuscular of 10 mg or 2 mg, up to QID, ziprasidone intramuscular 10 mg was statistically superior to ziprasidone intramuscular 2 mg, as assessed by AUC of the BARS at 0 to 2 hours, but not by CGI severity.

16 HOW SUPPLIED/STORAGE AND HANDLING

GEODON capsules are differentiated by capsule color/size and are imprinted in black ink with “Pfizer and ZDX [dosage strength]” or with “Pfizer” and a unique number. GEODON capsules are supplied for oral administration in 20 mg (blue/white), 40 mg (blue/blue), 60 mg (white/white), and 80 mg (blue/white) capsules. They are supplied in the following strengths and package configurations:

GEODON Capsules
Package; Configuration | Capsule; Strength (mg) | NDC (National Drug Code) | Imprint
Bottles of 60 | 20 | 0049-0052-60 or; 0049-0352-60 | ZDX 20
Bottles of 60 | 40 | 0049-0054-60 or; 0049-0354-60 | ZDX 40
Bottles of 60 | 60 | 0049-0056-60 or; 0049-0356-60 | ZDX 60
Bottles of 60 | 80 | 0049-0058-60 or; 0049-0358-60 | ZDX 80

or

GEODON Capsules
Package; Configuration | Capsule; Strength (mg) | NDC | Imprint
Bottles of 60 | 20 | 0049-3960-60 | 396
Bottles of 60 | 40 | 0049-3970-60 | 397
Bottles of 60 | 60 | 0049-3980-60 | 398
Bottles of 60 | 80 | 0049-3990-60 | 399

GEODON capsules should be stored at 25°C (77°F); excursions permitted to 15°C to 30°C (59°F to 86°F) [see USP Controlled Room Temperature].

GEODON for Injection is available in a single-dose vial as ziprasidone mesylate (20 mg ziprasidone/mL when reconstituted according to label instructions) [see Dosage and Administration (2.4)]. Each mL of ziprasidone mesylate for injection (when reconstituted) affords a colorless to pale pink solution that contains 20 mg of ziprasidone and 4.7 mg of methanesulfonic acid solubilized by 294 mg of sulfobutylether β-cyclodextrin sodium (SBECD).

GEODON for Injection
Package | Concentration | NDC
Single-dose Vials (carton of 10 vials) | 20 mg/mL | 0049-3920-10

GEODON for Injection should be stored at 25°C (77°F); excursions permitted to 15°C to 30°C (59°F to 86°F) [see USP Controlled Room Temperature] in dry form. Protect from light. Following reconstitution, GEODON for Injection can be stored, when protected from light, for up to 24 hours at 15°C to 30°C (59°F to 86°F) or up to 7 days refrigerated, 2°C to 8°C (36°F to 46°F).

17 PATIENT COUNSELING INFORMATION

Advise the patient to read the FDA-approved patient labeling (Patient Information).

Administration Information for Capsules

Advise patients to take GEODON capsules whole. Do not open, crush, or chew the capsules. Instruct patients to take GEODON capsules with food for optimal absorption. The absorption of ziprasidone is increased up to two-fold in the presence of food [see Dosage and Administration (2.1), Drug Interactions (7.10), and Clinical Pharmacology (12.3)].

QTc Prolongation

Advise patients to inform their health care providers of the following: History of QT prolongation; recent acute myocardial infarction; uncompensated heart failure; prescription of other drugs that have demonstrated QT prolongation; risk for significant electrolyte abnormalities; and history of cardiac arrhythmia [see Contraindications (4.1) and Warnings and Precautions (5.3)].

Instruct patients to report the onset of any conditions that put them at risk for significant electrolyte disturbances, hypokalemia in particular, including but not limited to the initiation of diuretic therapy or prolonged diarrhea. In addition, instruct patients to report symptoms such as dizziness, palpitations, or syncope to the prescriber [see Warnings and Precautions (5.3)].

Serotonin Syndrome

Caution patients about the risk of serotonin syndrome, particularly with the concomitant use of GEODON with other serotonergic drugs including SSRIs, SNRIs, triptans, tricyclic antidepressants, opioids, lithium, tryptophan, buspirone, amphetamines, St. John’s Wort, and with drugs that impair the metabolism of serotonin (in particular, MAOIs, which include those intended to treat psychiatric disorders and also others, such as linezolid). Instruct patients to contact their health care provider, or report to the emergency room, should they experience signs or symptoms of serotonin syndrome [see Contraindication (4.3), Warnings and Precautions (5.4), Drug Interactions (7.3)].

Severe Cutaneous Adverse Reactions

Instruct patients to report to their health care provider at the earliest onset any signs or symptoms that may be associated with Drug Reaction with Eosinophilia and Systemic Symptoms (DRESS) or with severe cutaneous adverse reactions, such as Stevens-Johnson syndrome [see Warnings and Precautions (5.6)].

Pregnancy

Advise pregnant women to notify their healthcare provider if they become pregnant or intend to become pregnant during treatment with GEODON. Advise patients that GEODON may cause extrapyramidal and/or withdrawal symptoms (agitation, hypertonia, hypotonia, tremor, somnolence, respiratory distress, and feeding disorder) in a neonate. Advise patients that there is a pregnancy exposure registry that monitors pregnancy outcomes in women exposed to GEODON during pregnancy [see Use in Specific Populations (8.1)].

Lactation

Advise breastfeeding women using GEODON to monitor infants for excess sedation, irritability, poor feeding, and extrapyramidal symptoms (tremors, and abnormal muscle movements) and to seek medical care if they notice these signs [see Use in Specific Populations (8.2)].

Infertility

Advise females of reproductive potential that GEODON may impair fertility due to an increase in serum prolactin levels. The effects on fertility are reversible [see Warnings and Precautions (5.15) and Use in Specific Populations (8.3)].

Distributed by:
Viatris Specialty LLC
Morgantown, WV 26505 U.S.A.

© 2024 Viatris Inc.

GEODON is a registered trademark of Viatris Specialty LLC, a Viatris Company.

The brands listed are trademarks of their respective owners.

UPJ:GDNCI:RX

PATIENT SUMMARY OF INFORMATION ABOUT

GEODON® Capsules
(ziprasidone)

Information for patients taking GEODON or their caregivers

This summary contains important information about GEODON. It is not meant to take the place of your doctor’s instructions. Read this information carefully before you take GEODON. Ask your doctor or pharmacist if you do not understand any of this information or if you want to know more about GEODON.

What Is GEODON?

GEODON is a type of prescription medicine called a psychotropic, also known as an atypical antipsychotic. GEODON can be used to treat symptoms of schizophrenia and acute manic or mixed episodes associated with bipolar disorder. GEODON can also be used as maintenance treatment of bipolar disorder when added to lithium or valproate.

Who Should Take GEODON?

Only your doctor can know if GEODON is right for you. GEODON may be prescribed for you if you are an adult with schizophrenia or bipolar disorder.

Symptoms of schizophrenia may include:

- hearing voices, seeing things, or sensing things that are not there (hallucinations)
- beliefs that are not true (delusions)
- unusual suspiciousness (paranoia)
- becoming withdrawn from family and friends

Symptoms of manic or mixed episodes of bipolar disorder may include:

- extremely high or irritable mood
- increased energy, activity, and restlessness
- racing thoughts or talking very fast
- easily distracted
- little need for sleep

If you show a response to GEODON, your symptoms may improve. If you continue to take GEODON there is less chance of your symptoms returning. Do not stop taking the capsules even when you feel better without first discussing it with your doctor.

It is also important to remember that GEODON capsules should be taken with food.

What is the most important safety information I should know about GEODON?

GEODON is not approved for the treatment of patients with dementia-related psychosis. Elderly patients with a diagnosis of psychosis related to dementia treated with antipsychotics are at an increased risk of death when compared to patients who are treated with placebo (a sugar pill).

GEODON is an effective drug to treat the symptoms of schizophrenia and the manic or mixed episodes of bipolar disorder. However, one potential side effect is that it may change the way the electrical current in your heart works more than some other drugs. The change is small and it is not known whether this will be harmful, but some other drugs that cause this kind of change have in rare cases caused dangerous heart rhythm abnormalities. Because of this, GEODON should be used only after your doctor has considered this risk for GEODON against the risks and benefits of other medications available for treating schizophrenia or bipolar manic and mixed episodes.

Your risk of dangerous changes in heart rhythm can be increased if you are taking certain other medicines and if you already have certain abnormal heart conditions. Therefore, it is important to tell your doctor about any other medicines that you take, including non-prescription medicines, supplements, and herbal medicines. You must also tell your doctor about any heart problems you have or have had.

Who should NOT take GEODON?

Elderly patients with a diagnosis of psychosis related to dementia. GEODON is not approved for the treatment of these patients.

Do not take GEODON if you:

- take anything that can increase the chance of a heart rhythm abnormality.
- have certain heart diseases, for example, long QT syndrome, a recent heart attack, severe heart failure, or certain irregularities of heart rhythm (discuss the specifics with your doctor).
- are currently taking medications that should not be taken in combination with ziprasidone, for example, dofetilide, sotalol, quinidine, other Class Ia and III anti-arrhythmics, mesoridazine, thioridazine, chlorpromazine, droperidol, pimozide, sparfloxacin, gatifloxacin, moxifloxacin, halofantrine, mefloquine, pentamidine, arsenic trioxide, levomethadyl acetate, dolasetron mesylate, probucol or tacrolimus.
- are taking a monoamine oxidase inhibitor (MAOI). Ask your healthcare provider or pharmacist if you are not sure if you take an MAOI, including linezolid or intravenous methylene blue.
- have stopped taking an MAOI in the last 14 days.
- are allergic to ziprasidone or any of the ingredients in GEODON.

What To Tell Your Doctor Before You Start GEODON

Only your doctor can decide if GEODON is right for you. Before you start GEODON, be sure to tell your doctor if you:

- have had any problem with the way your heart beats or any heart related illness or disease
- any family history of heart disease, including recent heart attack
- have had any problem with fainting or dizziness
- are taking or have recently taken any prescription medicines
- are taking any over-the-counter medicines you can buy without a prescription, including natural/herbal remedies
- have had any problems with your liver
- are pregnant, might be pregnant, or plan to get pregnant
- are breastfeeding or plan to breastfeed
- are allergic to any medicines
- have ever had an allergic reaction to ziprasidone or any of the other ingredients of GEODON capsules. Ask your doctor or pharmacist for a list of these ingredients
- have low levels of potassium or magnesium in your blood

Your doctor may want you to get additional laboratory tests to see if GEODON is an appropriate treatment for you.

GEODON And Other Medicines

There are some medications that may be unsafe to use when taking GEODON, and there are some medicines that can affect how well GEODON works. While you are on GEODON, check with your doctor before starting any new prescription or over-the-counter medications, including natural/herbal remedies.

How To Take GEODON

- Take GEODON only as directed by your doctor.
- Swallow GEODON capsules whole. Do not chew, crush, or open the capsules.
- Take GEODON capsules with food.
- It is best to take GEODON at the same time each day.
- GEODON may take a few weeks to work. It is important to be patient.
- Do not change your dose or stop taking your medicine without your doctor’s approval.
- Remember to keep taking your capsules, even when you feel better.

Possible Side Effects

Because these problems could mean you’re having a heart rhythm abnormality, contact your doctor IMMEDIATELY if you:

- Faint or lose consciousness
- Feel a change in the way that your heart beats (palpitations)

Common side effects of GEODON include the following and should also be discussed with your doctor if they occur:

Adults:

- Feeling unusually tired or sleepy
- Nausea or upset stomach
- Constipation
- Dizziness
- Restlessness
- Abnormal muscle movements, including tremor, shuffling, and uncontrolled involuntary movements
- Diarrhea
- Rash
- Increased cough / runny nose

If you develop any side effects that concern you, talk with your doctor. It is particularly important to tell your doctor if you have diarrhea, vomiting, or another illness that can cause you to lose fluids. Your doctor may want to check your blood to make sure that you have the right amount of important salts after such illnesses.

For a list of all side effects that have been reported, ask your doctor or pharmacist for the GEODON Professional Package Insert.

What To Do For An Overdose

In case of an overdose, call your doctor or poison control center right away or go to the nearest emergency room.

Other Important Safety Information

A potentially life-threatening problem called serotonin syndrome can happen when you take GEODON with certain other medicines.
See “Who should NOT take GEODON?”

- Call your healthcare provider if you have any of the following signs and symptoms of serotonin syndrome: agitation, hallucinations, coma, or other changes in mental status; racing heartbeat, high or low blood pressure; coordination problems or muscle twitching; nausea, vomiting, or diarrhea; sweating or fever; muscle rigidity.

A serious condition called neuroleptic malignant syndrome (NMS) can occur with all antipsychotic medications including GEODON. Signs of NMS include very high fever, rigid muscles, shaking, confusion, sweating, or increased heart rate and blood pressure. NMS is a rare but serious side effect that could be fatal. Therefore, tell your doctor if you experience any of these signs.

Delayed-onset drug reaction called drug reaction with eosinophilia and systemic symptoms (DRESS) can occur with ziprasidone. Signs of DRESS may include rash, fever, and swollen lymph nodes. Other severe cutaneous adverse reactions (SCAR), such as Stevens-Johnson syndrome can occur with ziprasidone. Signs of Stevens-Johnson syndrome may include rash with blisters which could include ulcers in mouth, skin shedding, fever and target-like spots in the skin. DRESS and other SCAR are sometimes fatal; therefore, tell your doctor immediately if you experience any of these signs.

Adverse reactions related to high blood sugar (hyperglycemia), sometimes serious, have been reported in patients treated with atypical antipsychotics. There have been few reports of hyperglycemia or diabetes in patients treated with GEODON, and it is not known if GEODON is associated with these reactions. Patients treated with an atypical antipsychotic should be monitored for symptoms of hyperglycemia.

Dizziness caused by a drop in your blood pressure may occur with GEODON, especially when you first start taking this medication or when the dose is increased. If this happens, be careful not to stand up too quickly, and talk to your doctor about the problem.

Before taking GEODON, tell your doctor if you

- are pregnant or plan on becoming pregnant.
  - If you become pregnant while receiving GEODON, talk to your healthcare provider about registering with the National Pregnancy Registry for Atypical Antipsychotics. You can register by calling 1-866-961-2388 or go to http://womensmentalhealth.org/clinical-and-research-programs/pregnancyregistry/
- are breastfeeding or plan to breastfeed. GEODON can pass into your breast milk. Talk to your healthcare provider about the best way to feed your baby if you receive GEODON.

Because GEODON can cause sleepiness, be careful when operating machinery or driving a motor vehicle.

Since medications of the same drug class as GEODON may interfere with the ability of the body to adjust to heat, it is best to avoid situations involving high temperature or humidity.

It is best to avoid consuming alcoholic beverages while taking GEODON.

Call your doctor immediately if you take more than the amount of GEODON prescribed by your doctor.

GEODON has not been shown to be safe or effective in the treatment of children and teenagers under the age of 18 years old.

Keep GEODON and all medicines out of the reach of children.

How To Store GEODON

Store GEODON capsules at room temperature (59°F to 86°F or 15°C to 30°C).

For More Information About GEODON

This sheet is only a summary. GEODON is a prescription medicine and only your doctor can decide if it is right for you. If you have any questions or want more information about GEODON, talk with your doctor or pharmacist.

Distributed by:
Viatris Specialty LLC
Morgantown, WV 26505 U.S.A.

© 2024 Viatris Inc.

GEODON is a registered trademark of Viatris Specialty LLC, a Viatris Company.

The brands listed are trademarks of their respective owners.

UPJ:PL:GDNCI:RX

Revised: 1/2025

PRINCIPAL DISPLAY PANEL - 20 mg Capsule Bottle Label

NDC 0049-3960-60

Pfizer

Geodon®
ziprasidone HCl

20 mg*

60 Capsules
Rx only

PRINCIPAL DISPLAY PANEL - 60 mg Capsule Bottle Label

NDC 0049-3980-60

Pfizer

Geodon®
ziprasidone HCl

60 mg*

60 Capsules
Rx only

PRINCIPAL DISPLAY PANEL - 80 mg Capsule Bottle Label

NDC 0049-3990-60

Pfizer

Geodon®
ziprasidone HCl

80 mg*

60 Capsules
Rx only

PRINCIPAL DISPLAY PANEL - 20 mg/mL Single Dose Vial Label

Single Dose Vial
NDC 0049-3920-20

Geodon®
for Injection
(ziprasidone mesylate)

equivalent to
20 mg/mL*
of ziprasidone

Sterile
For Intramuscular Use Only
Rx only

PRINCIPAL DISPLAY PANEL – 20 mg/mL Vial Carton

NDC 0049-3920-20

Single Dose Vial

Geodon®
for Injection

(ziprasidone mesylate)

equivalent to
20 mg/mL*
of ziprasidone

Sterile
For Intramuscular Use Only

Pfizer Injectables

Rx only

PRINCIPAL DISPLAY PANEL - 10 Vial Carton

NDC 0049-3920-83
Contains 10 of NDC 0049-3920-20

10 Single Dose Vials

Geodon® for Injection
(ziprasidone mesylate)

equivalent to
20 mg/mL*
of ziprasidone

Sterile
For Intramuscular Use Only

Pfizer Injectables

Rx only

PRINCIPAL DISPLAY PANEL - 20 mg/mL Vial Label - 0049-3920-01

NDC 0049-3920-01
Single Dose Vial

Geodon®
for Injection
(ziprasidone mesylate)
equivalent to
20 mg/mL*
of ziprasidone

PROTECT FROM LIGHT.

Sterile
For Intramuscular Use Only
Rx only

PRINCIPAL DISPLAY PANEL - 20 mg/mL Vial Carton - 0049-3920-10

10 Single Dose Vials
NDC 0049-3920-10
Contains 10 of NDC 0049-3920-01

Geodon® for Injection
(ziprasidone mesylate)

equivalent to
20 mg/mL*
of ziprasidone

PROTECT FROM LIGHT.

Sterile
For Intramuscular Use Only

Pfizer Injectables
Rx only

PRINCIPAL DISPLAY PANEL - 20 mg Capsule Bottle Label - 0052

NDC 0049-0052-60

Pfizer

Geodon®
(ziprasidone HCl)
capsules

20 mg*

60 Capsules
Rx only

PRINCIPAL DISPLAY PANEL - 40 mg Capsule Bottle Label - 0054

NDC 0049-0054-60

Pfizer

Geodon®
(ziprasidone HCl)
capsules

40 mg*

60 Capsules
Rx only

PRINCIPAL DISPLAY PANEL - 60 mg Capsule Bottle Label - 0056

NDC 0049-0056-60

Pfizer

Geodon®
(ziprasidone HCl)
capsules

60 mg*

60 Capsules
Rx only

PRINCIPAL DISPLAY PANEL - 80 mg Capsule Bottle Label - 0058

NDC 0049-0058-60

Pfizer

Geodon®
(ziprasidone HCl)
capsules

80 mg*

60 Capsules
Rx only

PRINCIPAL DISPLAY PANEL - 20 mg Capsule Bottle Label - 0352

NDC 0049-0352-60

Pfizer

Geodon®
(ziprasidone)
capsules

20 mg*

60 Capsules
Rx only

PRINCIPAL DISPLAY PANEL - 40 mg Capsule Bottle Label - 0354

NDC 0049-0354-60

Pfizer

Geodon®
(ziprasidone)
capsules

40 mg*

60 Capsules
Rx only

PRINCIPAL DISPLAY PANEL - 60 mg Capsule Bottle Label - 0356

NDC 0049-0356-60

Pfizer

Geodon®
(ziprasidone)
capsules

60 mg*

60 Capsules
Rx only

PRINCIPAL DISPLAY PANEL - 80 mg Capsule Bottle Label - 0358

NDC 0049-0358-60

Pfizer

Geodon®
(ziprasidone)
capsules

80 mg*

60 Capsules
Rx only